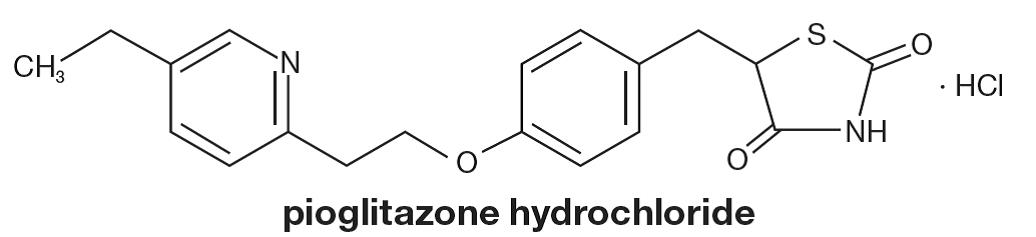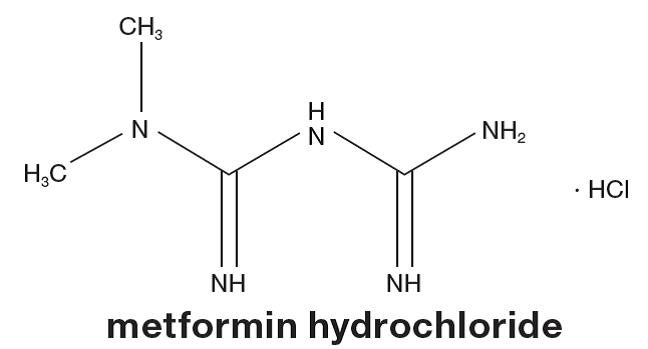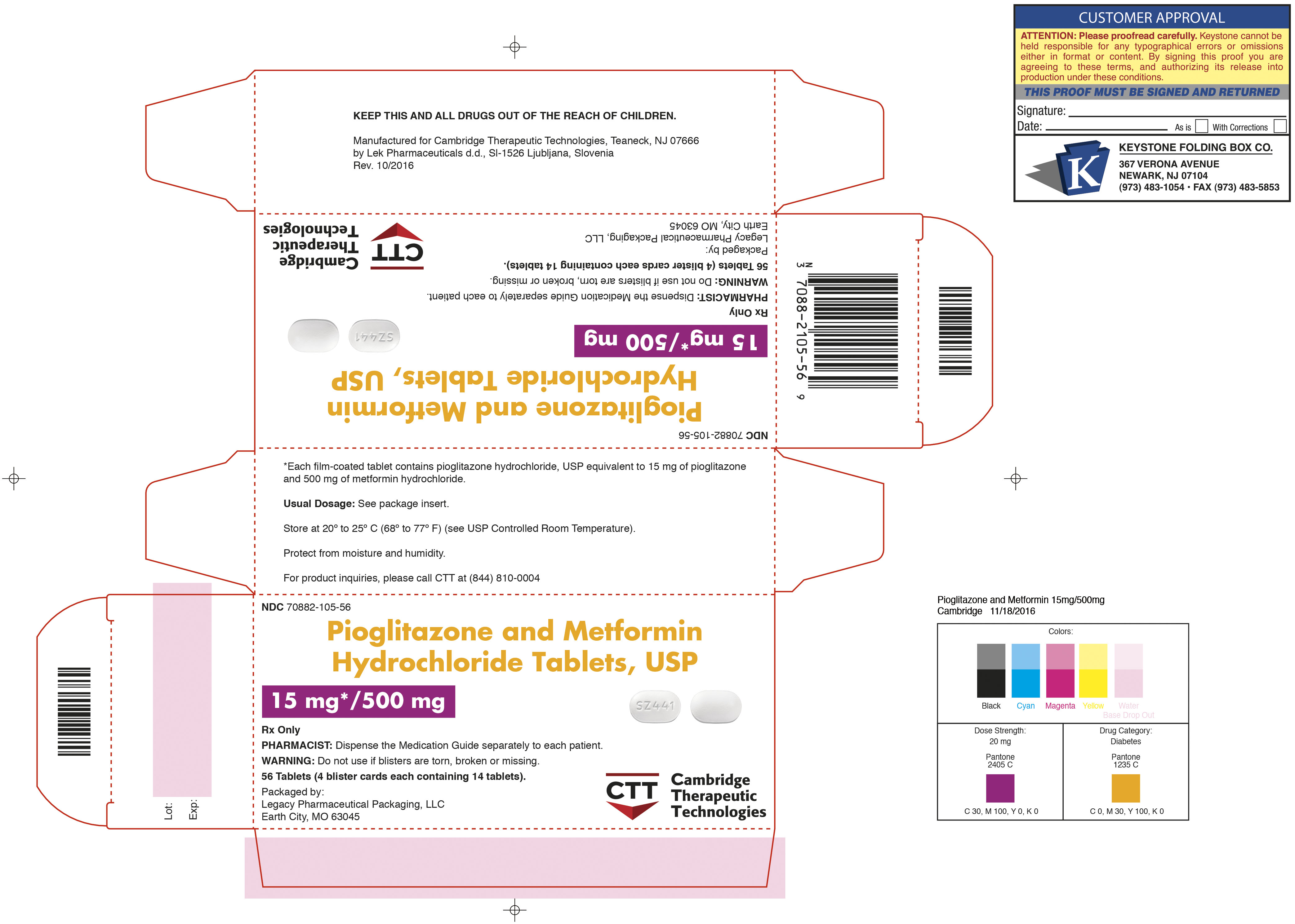 DRUG LABEL: Pioglitazone and metformin
NDC: 70882-105 | Form: TABLET, FILM COATED
Manufacturer: Cambridge Therapeutics Technologies, LLC
Category: prescription | Type: HUMAN PRESCRIPTION DRUG LABEL
Date: 20161123

ACTIVE INGREDIENTS: PIOGLITAZONE HYDROCHLORIDE 15 mg/1 1; METFORMIN HYDROCHLORIDE 500 mg/1 1
INACTIVE INGREDIENTS: CROSCARMELLOSE SODIUM; HYDROXYPROPYL CELLULOSE (TYPE H); HYPROMELLOSE 2910 (6 MPA.S); MAGNESIUM STEARATE; CELLULOSE, MICROCRYSTALLINE; POLYETHYLENE GLYCOL 6000; POVIDONE K25; TALC; TITANIUM DIOXIDE

HIGHLIGHTS OF PRESCRIBING INFORMATION

These highlights do not include all the information needed to use PIOGLITAZONE and METFORMIN HYDROCHLORIDE TABLETS safely and effectively. See full prescribing information for PIOGLITAZONE and METFORMIN HYDROCHLORIDE TABLETS.
PIOGLITAZONE and METFORMIN HYDROCHLORIDE tablets, for oral use
Initial U.S. Approval: 2005

WARNING: CONGESTIVE HEART FAILURE AND LACTIC ACIDOSIS

See full prescribing information for complete boxed warning

Congestive Heart Failure

- •Thiazolidinediones, including pioglitazone, which is a component of pioglitazone and metformin hydrochloride, cause or exacerbate congestive heart failure in some patients. (5.1)
- •After initiation of pioglitazone and metformin hydrochloride, and after dose increases, monitor patients carefully for signs and symptoms of heart failure (e.g., excessive, rapid weight gain, dyspnea, and/or edema). If heart failure develops, it should be managed according to current standards of care and discontinuation or dose reduction of pioglitazone and metformin hydrochloride must be considered. (5.1)
- •Pioglitazone and metformin hydrochloride is not recommended in patients with symptomatic heart failure.
- •Initiation of pioglitazone and metformin hydrochloride in patients with established New York Heart Association (NYHA) Class III or IV heart failure is contraindicated. (4, 5.1)

Lactic Acidosis

- •Lactic acidosis can occur due to metformin accumulation. The risk increases with conditions such as sepsis, dehydration, excess alcohol intake, hepatic impairment, renal impairment, and acute congestive heart failure. (5.2)
- •Symptoms include malaise, myalgias, respiratory distress, increasing somnolence, and nonspecific abdominal distress. Laboratory abnormalities include low pH, increased anion gap, and elevated blood lactate. (5.2)
- •If acidosis is suspected, discontinue pioglitazone and metformin hydrochloride and hospitalize the patient immediately. (5.2)

1 INDICATIONS AND USAGE

Pioglitazone and metformin hydrochloride tablets are a thiazolidinedione and biguanide combination product indicated as an adjunct to diet and exercise to improve glycemic control in adults with type 2 diabetes mellitus when treatment with both pioglitazone and metformin is appropriate. (1, 14)

Important Limitations of Use:

- •Not for treatment of type 1 diabetes or diabetic ketoacidosis. (1)

2 DOSAGE AND ADMINISTRATION

- •Individualize the starting dose of pioglitazone and metformin hydrochloride tablets based on the patient's current regimen. (2)
- •May adjust the dosing based on effectiveness and tolerability while not exceeding the maximum recommended daily dose of pioglitazone 45 mg and metformin 2550 mg. (2)
- •Pioglitazone and metformin hydrochloride tablets should be given in divided daily doses with meals to reduce the gastrointestinal (GI) side effects due to metformin. (2)
- •Dose increases should be accompanied by careful monitoring for adverse events related to fluid retention. (2)
- •Obtain liver tests before starting pioglitazone and metformin hydrochloride tablets. If abnormal, use caution when treating with pioglitazone and metformin hydrochloride tablets, investigate the probable cause, treat (if possible), and follow appropriately. Monitoring liver tests while on pioglitazone and metformin hydrochloride tablets is not recommended in patients without liver disease. (5.5)

3 DOSAGE FORMS AND STRENGTHS

Tablets: 15 mg pioglitazone/500 mg metformin hydrochloride and 15 mg pioglitazone/850 mg metformin hydrochloride (3)

4 CONTRAINDICATIONS

- •Initiation in patients with established New York Heart Association (NYHA) Class III or IV heart failure [see Boxed Warning]. (4)
- •Renal impairment. (4)
- •Use in patients with known hypersensitivity to pioglitazone, metformin or any other component of pioglitazone and metformin hydrochloride. (4)
- •Metabolic acidosis, including diabetic ketoacidosis. (4, 5.2)

5 WARNINGS AND PRECAUTIONS

- •Congestive heart failure: Fluid retention may occur and can exacerbate or lead to congestive heart failure. Combination use with insulin and use in congestive heart failure NYHA Class I and II may increase risk. Monitor patients for signs and symptoms. (5.1)
- •Lactic acidosis: Warn against excessive alcohol intake. Pioglitazone and metformin hydrochloride is not recommended in hepatic impairment and is contraindicated in renal impairment. Ensure normal renal function before initiating and at least annually thereafter. (5.2, 5.10)
- •Edema: Dose-related edema may occur. (5.3)
- •Hypoglycemia: When used with insulin or an insulin secretagogue, a lower dose of the insulin or insulin secretagogue may be needed to reduce the risk of hypoglycemia. (5.4)
- •Hepatic effects: Postmarketing reports of hepatic failure, sometimes fatal. Causality cannot be excluded. If liver injury is detected, promptly interrupt pioglitazone and metformin hydrochloride and assess patient for probable cause, then treat cause if possible, to resolution or stabilization. Do not restart pioglitazone and metformin hydrochloride if liver injury is confirmed and no alternate etiology can be found. (5.5)
- •Bladder cancer: Preclinical and clinical trial data, and results from an observational study suggest an increased risk of bladder cancer in pioglitazone users. The observational data further suggest that the risk increases with duration of use. Do not use in patients with active bladder cancer. Use caution when using in patients with a prior history of bladder cancer. (5.6)
- •Fractures: Increased incidence in female patients. Apply current standards of care for assessing and maintaining bone health. (5.7)
- •Macular edema: Postmarketing reports. Recommend regular eye exams in all patients with diabetes according to current standards of care with prompt evaluation for acute visual changes. (5.8)
- •Temporarily discontinue in patients undergoing radiologic studies with intravascular iodinated contrast materials or any surgical procedures necessitating restricted intake of food and fluids. (5.12)
- •Vitamin B12 deficiency: Metformin may lower vitamin B12 levels. Monitor hematologic parameters annually. (5.14)
- •Macrovascular outcomes: There have been no clinical studies establishing conclusive evidence of macrovascular risk reduction with pioglitazone and metformin hydrochloride or any other antidiabetic drug. (5.15)

6 ADVERSE REACTIONS

Most common adverse reactions (>5%) are upper respiratory tract infection, edema, diarrhea, headache and weight gain. (6.1)

To report SUSPECTED ADVERSE REACTIONS, contact Cambridge Therapeutic Technologies, LLC at 1-844-810-0004 or FDA at 1-800-FDA-1088 or www.fda.gov/medwatch.

7 DRUG INTERACTIONS

- •Strong CYP2C8 inhibitors (e.g., gemfibrozil) increase pioglitazone concentrations. Limit pioglitazone and metformin hydrochloride dose to 15 mg/850 mg daily. (2.3, 7.1)
- •CYP2C8 inducers (e.g., rifampin) may decrease pioglitazone concentrations. (7.2)
- •Cationic drugs: May reduce metformin elimination. Use with caution in patients who are taking cationic medications eliminated by renal tubular secretion. (7.4)

8 USE IN SPECIFIC POPULATIONS

- •Nursing mothers: Discontinue drug or nursing, taking into consideration the importance of the drug to the mother. (8.3)
- •Pediatrics: Not recommended for use in pediatric patients. (8.4)

FULL PRESCRIBING INFORMATION

WARNING: CONGESTIVE HEART FAILURE AND LACTIC ACIDOSIS

Congestive Heart Failure

- •Thiazolidinediones, including pioglitazone, which is a component of pioglitazone and metformin hydrochloride, cause or exacerbate congestive heart failure in some patients [see WARNINGS AND PRECAUTIONS (5.1)].
- •After initiation of pioglitazone and metformin hydrochloride, and after dose increases, monitor patients carefully for signs and symptoms of heart failure (e.g., excessive, rapid weight gain, dyspnea, and/or edema). If heart failure develops, it should be managed according to current standards of care and discontinuation or dose reduction of pioglitazone and metformin hydrochloride must be considered [see WARNINGS AND PRECAUTIONS (5.1)].
- •Pioglitazone hydrochloride and metformin hydrochloride is not recommended in patients with symptomatic heart failure.
- •Initiation of pioglitazone and metformin hydrochloride in patients with established New York Heart Association (NYHA) Class III or IV heart failure is contraindicated [see CONTRAINDICATIONS (4) and WARNINGS AND PRECAUTIONS (5.1)].

Lactic Acidosis

- •Lactic acidosis is a rare but serious complication that can occur due to metformin accumulation. The risk increases with conditions such as sepsis, dehydration, excess alcohol intake, hepatic impairment, renal impairment, and acute congestive heart failure [see WARNINGS AND PRECAUTIONS (5.2)].
- •The onset is often subtle, accompanied only by nonspecific symptoms such as malaise, myalgias, respiratory distress, increasing somnolence, and nonspecific abdominal distress. Laboratory abnormalities include low pH, increased anion gap, and elevated blood lactate [see WARNINGS AND PRECAUTIONS (5.2)].
- •If acidosis is suspected, pioglitazone and metformin hydrochloride should be discontinued and the patient hospitalized immediately [see WARNINGS AND PRECAUTIONS (5.2)].

1 INDICATIONS AND USAGE

Pioglitazone and metformin hydrochloride tablets are indicated as an adjunct to diet and exercise to improve glycemic control in adults with type 2 diabetes mellitus when treatment with both pioglitazone and metformin is appropriate [see CLINICAL STUDIES (14)].

Important Limitations of Use

Pioglitazone exerts its antihyperglycemic effect only in the presence of endogenous insulin. Pioglitazone and metformin hydrochloride tablets should not be used to treat type 1 diabetes or diabetic ketoacidosis, as it would not be effective in these settings.

Use caution in patients with liver disease [see WARNINGS AND PRECAUTIONS (5.5)].

2 DOSAGE AND ADMINISTRATION

2.1 Recommendations for All Patients

Pioglitazone and metformin hydrochloride tablets should be taken with meals to reduce the gastrointestinal side effects associated with metformin.

If therapy with a combination tablet containing pioglitazone and metformin is considered appropriate the recommended starting dose is:

- •15 mg/500 mg twice daily or 15 mg/850 mg once daily and gradually titrated, as needed, after assessing adequacy of therapeutic response and tolerability,
- •for patients with New York Heart Association (NYHA) Class I or Class II congestive heart failure: 15 mg/500 mg or 15 mg/850 mg once daily and gradually titrated, as needed, after assessing adequacy of therapeutic response and tolerability,
- •for patients inadequately controlled on metformin monotherapy: 15 mg/500 mg twice daily or 15 mg/850 mg once or twice daily (depending on the dose of metformin already being taken) and gradually titrated, as needed, after assessing adequacy of therapeutic response and tolerability,
- •for patients inadequately controlled on pioglitazone monotherapy: 15 mg/500 mg twice daily or 15 mg/850 mg once daily and gradually titrated, as needed, after assessing adequacy of therapeutic response and tolerability,
- •for patients who are changing from combination therapy of pioglitazone plus metformin as separate tablets: Pioglitazone and metformin hydrochloride tablets should be taken at doses that are as close as possible to the dose of pioglitazone and metformin already being taken.

Pioglitazone and metformin hydrochloride tablets may be titrated up to a maximum daily dose of 45 mg of pioglitazone and 2550 mg of metformin.

Metformin doses above 2000 mg may be better tolerated given 3 times a day.

After initiation of pioglitazone and metformin hydrochloride tablets or with dose increase, monitor patients carefully for adverse reactions related to fluid retention such as weight gain, edema, and signs and symptoms of congestive heart failure [see Boxed Warning and WARNINGS AND PRECAUTIONS (5.1)]. Liver tests (serum alanine and aspartate aminotransferases, alkaline phosphatase, and total bilirubin) should be obtained prior to initiating pioglitazone and metformin hydrochloride tablets. Routine periodic monitoring of liver tests during treatment with pioglitazone and metformin hydrochloride tablets are not recommended in patients without liver disease. Patients who have liver test abnormalities prior to initiation of pioglitazone and metformin hydrochloride tablets or who are found to have abnormal liver tests while taking pioglitazone and metformin hydrochloride tablets should be managed as described under Warnings and Precautions [see WARNINGS AND PRECAUTIONS (5.5) and CLINICAL PHARMACOLOGY (12.3)].

2.2 Concomitant Use with an Insulin Secretagogue or Insulin

If hypoglycemia occurs in a patient coadministered pioglitazone and metformin hydrochloride tablets and an insulin secretagogue (e.g., sulfonylurea), the dose of the insulin secretagogue should be reduced.

If hypoglycemia occurs in a patient co-administered pioglitazone and metformin hydrochloride tablets and insulin, the dose of insulin should be decreased by 10% to 25%. Further adjustments to the insulin dose should be individualized based on glycemic response.

2.3 Concomitant Use with Strong CYP2C8 Inhibitors

Coadministration of pioglitazone (one of the ingredients in pioglitazone and metformin hydrochloride tablets) and gemfibrozil, a strong CYP2C8 inhibitor, increases pioglitazone exposure approximately 3-fold. Therefore, the maximum recommended dose of pioglitazone and metformin hydrochloride tablets are 15 mg/850 mg daily when used in combination with gemfibrozil or other strong CYP2C8 inhibitors [see DRUG INTERACTIONS (7.1) and CLINICAL PHARMACOLOGY (12.3)].

3 DOSAGE FORMS AND STRENGTHS

- 15 mg/500 mg tablets are white, oval, biconvex, film-coated tablets with “SZ441” on one side

4 CONTRAINDICATIONS

- •Initiation in patients with established NYHA Class III or IV heart failure [see Boxed Warning].
- •Renal impairment (e.g., serum creatinine levels ≥1.5 mg/dL [males], ≥1.4 mg/dL [females], or abnormal creatinine clearance) which may also result from conditions such as cardiovascular collapse (shock), acute myocardial infarction, and septicemia [see WARNINGS AND PRECAUTIONS (5.2, 5.10)].
- •Use in patients with known hypersensitivity to pioglitazone, metformin, or any other component of pioglitazone and metformin hydrochloride.
- •Metabolic acidosis, including diabetic ketoacidosis. Diabetic ketoacidosis should be treated with insulin.

5 WARNINGS AND PRECAUTIONS

5.1 Congestive Heart Failure

Pioglitazone

Pioglitazone, like other thiazolidinediones, can cause dose-related fluid retention when used alone or in combination with other antidiabetic medications and is most common when pioglitazone is used in combination with insulin. Fluid retention may lead to or exacerbate congestive heart failure. Patients treated with pioglitazone and metformin hydrochloride should be observed for signs and symptoms of congestive heart failure. If congestive heart failure develops, it should be managed according to current standards of care and discontinuation or dose reduction of pioglitazone and metformin hydrochloride must be considered [see BOXED WARNING, CONTRAINDICATIONS (4), and ADVERSE REACTIONS (6.1)].

5.2 Lactic Acidosis

Metformin hydrochloride

Lactic Acidosis

Lactic acidosis is a serious, metabolic complication that can occur due to metformin accumulation during treatment with pioglitazone and metformin hydrochloride and it is fatal in approximately 50% of cases. Lactic acidosis may also occur in association with a number of pathophysiologic conditions, including diabetes mellitus, and whenever there is significant tissue hypoperfusion and hypoxemia. Lactic acidosis is characterized by elevated blood lactate concentrations (>5 mmol/L), decreased blood pH, electrolyte disturbances with an increased anion gap, and an increased lactate/pyruvate ratio. When metformin is implicated as the cause of lactic acidosis, metformin plasma levels >5 mcg/mL are generally found.

The reported incidence of lactic acidosis in patients receiving metformin hydrochloride is approximately 0.03 cases/1000 patient-years, with approximately 0.015 fatal cases/1000 patient-years. In more than 20,000 patient-years, exposure to metformin in clinical trials, there were no reports of lactic acidosis. Reported cases have occurred primarily in diabetic patients with significant renal impairment, including both intrinsic renal disease and renal hypoperfusion, often in the setting of multiple concomitant medical/surgical problems and multiple concomitant medications. Patients with congestive heart failure requiring pharmacologic management, particularly when accompanied by hypoperfusion and hypoxemia, are at increased risk of lactic acidosis. The risk of lactic acidosis increases with the degree of renal dysfunction and the patient's age. The risk of lactic acidosis may, therefore, be significantly decreased by regular monitoring of renal function in patients taking metformin. In particular, treatment of the elderly should be accompanied by careful monitoring of renal function. Pioglitazone and metformin hydrochloride treatment should not be initiated in any patient unless measurement of creatinine clearance demonstrates that renal function is not reduced. In addition, metformin should be promptly withheld in the presence of any condition associated with hypoxemia, dehydration, or sepsis. Because impaired hepatic function may significantly limit the ability to clear lactate, metformin should generally be avoided in patients with clinical or laboratory evidence of hepatic impairment. Patients should be cautioned against excessive alcohol intake when taking metformin, because alcohol potentiates the effects of metformin on lactate metabolism. In addition, metformin should be temporarily discontinued prior to any intravascular radiocontrast study and for any surgical procedure necessitating restricted intake of food or fluids [see WARNINGS AND PRECAUTIONS (5.10, 5.11, 5.12, 5.13)]. Use of topiramate, a carbonic anhydrase inhibitor, in epilepsy and migraine prophylaxis may frequently cause dose-dependent metabolic acidosis and may exacerbate the risk of metformin-induced lactic acidosis [see DRUG INTERACTIONS (7.1) and CLINICAL PHARMACOLOGY (12.3)].

The onset of lactic acidosis often is subtle, and accompanied only by nonspecific symptoms such as malaise, myalgias, respiratory distress, increasing somnolence, and nonspecific abdominal distress. There may be associated hypothermia, hypotension, and resistant bradyarrhythmias with more marked acidosis. Patients should be educated to promptly report these symptoms should they occur. If present, pioglitazone and metformin hydrochloride should be withdrawn until lactic acidosis is ruled out. Serum electrolytes, ketones, blood glucose, blood pH, lactate levels, and blood metformin levels may be useful. Once a patient is stabilized on any dose level of metformin, gastrointestinal symptoms, which are common during initiation of therapy, are unlikely to recur. Later occurrence of gastrointestinal symptoms could be due to lactic acidosis or other serious disease.

Levels of fasting venous plasma lactate above the upper limit of normal but less than 5 mmol/L in patients taking metformin do not necessarily indicate impending lactic acidosis and may be explainable by other mechanisms, such as poorly controlled diabetes or obesity, vigorous physical activity, or technical problems in sample handling [see WARNINGS AND PRECAUTIONS (5.10)].

Lactic acidosis should be suspected in any diabetic patient with metabolic acidosis lacking evidence of ketoacidosis (ketonuria and ketonemia).

Lactic acidosis is a medical emergency that must be treated in a hospital setting. In a patient with lactic acidosis who is taking metformin, the drug should be discontinued immediately and general supportive measures promptly instituted. Because metformin hydrochloride is dialyzable (with a clearance of up to 170 mL/min under good hemodynamic conditions), prompt hemodialysis is recommended to correct the acidosis and remove the accumulated metformin. Such management often results in prompt reversal of symptoms and recovery [see CONTRAINDICATIONS (4) and WARNINGS AND PRECAUTIONS (5.10)].

5.3 Edema

In controlled clinical trials with pioglitazone, edema was reported more frequently in patients treated with pioglitazone than in placebo-treated patients and is dose related [see ADVERSE REACTIONS (6.1)]. In postmarketing experience, reports of new onset or worsening of edema have been received.

Pioglitazone and metformin hydrochloride should be used with caution in patients with edema. Because thiazolidinediones, including pioglitazone, can cause fluid retention, which can exacerbate or lead to congestive heart failure, pioglitazone and metformin hydrochloride should be used with caution in patients at risk for congestive heart failure. Patients treated with pioglitazone and metformin hydrochloride should be monitored for signs and symptoms of congestive heart failure [see Boxed Warning, WARNINGS AND PRECAUTIONS (5.1), and PATIENT COUNSELING INFORMATION (17.1)].

5.4 Hypoglycemia

Patients receiving pioglitazone and metformin hydrochloride in combination with insulin or other antidiabetic medications (particularly insulin secretagogues such as sulfonylureas) may be at risk for hypoglycemia. A reduction in the dose of the concomitant antidiabetic medication may be necessary to reduce the risk of hypoglycemia[see DOSAGE AND ADMINISTRATION (2.2)].

Hypoglycemia can also occur when caloric intake is deficient or when strenuous exercise is not compensated by caloric supplement. Elderly, debilitated, or malnourished patients, and those with adrenal or pituitary insufficiency or alcohol intoxication are particularly susceptible to hypoglycemic effects. Hypoglycemia may be difficult to recognize in the elderly, and in people who are taking beta-adrenergic blocking drugs.

5.5 Hepatic Effects

There have been postmarketing reports of fatal and nonfatal hepatic failure in patients taking pioglitazone, although the reports contain insufficient information necessary to establish the probable cause. There has been no evidence of drug-induced hepatotoxicity in the pioglitazone controlled clinical trial database to date [see ADVERSE REACTIONS (6.1)].

Patients with type 2 diabetes may have fatty liver disease or cardiac disease with episodic congestive heart failure, both of which may cause liver test abnormalities, and they may also have other forms of liver disease, many of which can be treated or managed. Therefore, obtaining a liver test panel (serum alanine aminotransferase [ALT], aspartate aminotransferase [AST], alkaline phosphatase, and total bilirubin) and assessing the patient is recommended before initiating pioglitazone and metformin hydrochloride therapy.

In patients with abnormal liver tests, pioglitazone and metformin hydrochloride should be initiated with caution.

Measure liver tests promptly in patients who report symptoms that may indicate liver injury, including fatigue, anorexia, right upper abdominal discomfort, dark urine or jaundice. In this clinical context, if the patient is found to have abnormal liver tests (ALT greater than three times the upper limit of the reference range), pioglitazone and metformin hydrochloride treatment should be interrupted and investigation done to establish the probable cause. Pioglitazone and metformin hydrochloride should not be restarted in these patients without another explanation for the liver test abnormalities.

Patients who have serum ALT greater than three times the reference range with serum total bilirubin greater than two times the reference range without alternative etiologies are at risk for severe drug-induced liver injury, and should not be restarted on pioglitazone and metformin hydrochloride. For patients with lesser elevations of serum ALT or bilirubin and with an alternate probable cause, treatment with pioglitazone and metformin hydrochloride can be used with caution.

Because impaired hepatic function has been associated with some cases of lactic acidosis pioglitazone and metformin hydrochloride should generally be avoided in patients with clinical or laboratory evidence of hepatic disease.

5.6 Urinary Bladder Tumors

Tumors were observed in the urinary bladder of male rats in the two-year carcinogenicity study [see NONCLINICAL TOXICOLOGY (13.1)]. In two 3-year trials in which pioglitazone was compared to placebo or glyburide, there were 16/3,656 (0.44%) reports of bladder cancer in patients taking pioglitazone compared to 5/3,679 (0.14%) in patients not taking pioglitazone. After excluding patients in whom exposure to study drug was less than one year at the time of diagnosis of bladder cancer, there were six (0.16%) cases on pioglitazone and two (0.05%) cases on placebo.

A five-year interim report of an ongoing 10-year observational cohort study found a nonsignificant increase in the risk for bladder cancer in subjects ever exposed to pioglitazone, compared to subjects never exposed to pioglitazone (HR 1.2 [95% CI 0.9 to 1.5]). Compared to never exposure, a duration of pioglitazone therapy longer than 12 months was associated with an increase in risk (HR 1.4 [95% CI 0.9 to 2.1]), which reached statistical significance after more than 24 months of pioglitazone use (HR 1.4 [95% CI 1.03 to 2]). Interim results from this study suggested that taking pioglitazone longer than 12 months increased the relative risk of developing bladder cancer in any given year by 40%, which equates to an absolute increase of 3 cases in 10,000 (from approximately 7 in 10,000 [without pioglitazone] to approximately 10 in 10,000 [with pioglitazone]).

There are insufficient data to determine whether pioglitazone is a tumor promoter for urinary bladder tumors. Consequently, pioglitazone and metformin hydrochloride should not be used in patients with active bladder cancer and the benefits of glycemic control versus unknown risks for cancer recurrence with pioglitazone and metformin hydrochloride should be considered in patients with a prior history of bladder cancer.

5.7 Fractures

In PROactive (the Prospective Pioglitazone Clinical Trial in Macrovascular Events), 5,238 patients with type 2 diabetes and a history of macrovascular disease were randomized to pioglitazone (N=2,605), force-titrated up to 45 mg daily or placebo (N=2,633) in addition to standard of care. During a mean follow-up of 34.5 months, the incidence of bone fracture in females was 5.1% (44/870) for pioglitazone versus 2.5% (23/905) for placebo. This difference was noted after the first year of treatment and persisted during the course of the study. The majority of fractures observed in female patients were nonvertebral fractures including lower limb and distal upper limb. No increase in the incidence of fracture was observed in men treated with pioglitazone (1.7%) versus placebo (2.1%). The risk of fracture should be considered in the care of patients, especially female patients, treated with pioglitazone and metformin hydrochloride and attention should be given to assessing and maintaining bone health according to current standards of care.

5.8 Macular Edema

Macular edema has been reported in postmarketing experience in diabetic patients who were taking pioglitazone or another thiazolidinedione. Some patients presented with blurred vision or decreased visual acuity, but others were diagnosed on routine ophthalmologic examination.

Most patients had peripheral edema at the time macular edema was diagnosed. Some patients had improvement in their macular edema after discontinuation of the thiazolidinedione.

Patients with diabetes should have regular eye exams by an ophthalmologist according to current standards of care. Patients with diabetes who report any visual symptoms should be promptly referred to an ophthalmologist, regardless of the patient's underlying medications or other physical findings [see ADVERSE REACTIONS (6.1)].

5.9 Ovulation

Therapy with pioglitazone, like other thiazolidinediones, may result in ovulation in some premenopausal anovulatory women. As a result, these patients may be at an increased risk for pregnancy while taking pioglitazone and metformin hydrochloride [see USE IN SPECIFIC POPULATIONS (8.1)]. This effect has not been investigated in clinical trials, so the frequency of this occurrence is not known. Adequate contraception in all premenopausal women treated with pioglitazone and metformin hydrochloride is recommended.

5.10 Monitoring of Renal Function

Metformin is substantially excreted by the kidney, and the risk of metformin accumulation and lactic acidosis increases with the degree of impairment of renal function. Therefore, pioglitazone and metformin hydrochloride is contraindicated in patients with renal impairment.

Before initiation of therapy with pioglitazone and metformin hydrochloride and at least annually thereafter, renal function should be assessed and verified as normal. In patients in whom development of renal dysfunction is anticipated (e.g., elderly), renal function should be assessed more frequently and pioglitazone and metformin hydrochloride discontinued if evidence of renal impairment is present.

Use of Concomitant Medications That May Affect Renal Function or Metformin Disposition

Concomitant medication(s) that may affect renal function or result in significant hemodynamic change or may interfere with the disposition of metformin, such as cationic drugs that are eliminated by renal tubular secretion, should be used with caution [see CLINICAL PHARMACOLOGY (12.3)].

Radiological Studies and Surgical Procedures

Radiologic studies involving the use of intravascular iodinated contrast materials (for example, intravenous urogram, intravenous cholangiography, angiography, and computed tomography (CT) scans with intravascular contrast materials) can lead to acute alteration of renal function and have been associated with lactic acidosis in patients receiving metformin [see CONTRAINDICATIONS (4)]. Therefore, in patients in whom any such study is planned, pioglitazone and metformin hydrochloride should be discontinued at the time of or prior to the procedure, and withheld for 48 hours subsequent to the procedure and reinstituted only after renal function has been re-evaluated and found to be normal.

5.11 Hypoxic States

Cardiovascular collapse (shock) from whatever cause, acute congestive heart failure, acute myocardial infarction and other conditions characterized by hypoxemia have been associated with lactic acidosis and may also cause prerenal azotemia. When such events occur in patients receiving pioglitazone and metformin hydrochloride therapy, the drug should be promptly discontinued.

5.12 Surgical Procedures

Use of pioglitazone and metformin hydrochloride should be temporarily suspended for any surgical procedure (except minor procedures not associated with restricted intake of food and fluids) and should not be restarted until the patient's oral intake has resumed and renal function has been evaluated as normal.

5.13 Alcohol Intake

Alcohol is known to potentiate the effect of metformin on lactate metabolism. Patients, therefore, should be warned against excessive alcohol intake, acute or chronic, while receiving pioglitazone and metformin hydrochloride.

5.14 Vitamin B12 Levels

In controlled clinical trials of metformin of 29 weeks’ duration, a decrease to subnormal levels of previously normal serum vitamin B12 levels, without clinical manifestations, was observed in approximately 7% of patients. Such decrease, possibly due to interference with B12 absorption from the B12-intrinsic factor complex, is, however, very rarely associated with anemia and appears to be rapidly reversible with discontinuation of metformin or vitamin B12 supplementation. Measurement of hematologic parameters on an annual basis is advised in patients on pioglitazone and metformin hydrochloride and any apparent abnormalities should be appropriately investigated and managed. Certain individuals (those with inadequate vitamin B12 or calcium intake or absorption) appear to be predisposed to developing subnormal vitamin B12 levels. In these patients, routine serum vitamin B12 measurements at two- to three-year intervals may be useful.

5.15 Macrovascular Outcomes

There have been no clinical studies establishing conclusive evidence of macrovascular risk reduction with pioglitazone and metformin hydrochloride or any other oral antidiabetic drug.

6 ADVERSE REACTIONS

The following serious adverse reactions are discussed elsewhere in the labeling:

- •Congestive heart failure [see BOXED WARNING and WARNINGS AND PRECAUTIONS (5.1)]
- •Lactic acidosis [see BOXED WARNING and WARNINGS AND PRECAUTIONS (5.2)]
- •Edema [see WARNINGS AND PRECAUTIONS (5.3)]
- •Fractures [see WARNINGS AND PRECAUTIONS (5.7)]

6.1 Clinical Trials Experience

Because clinical trials are conducted under widely varying conditions, adverse reaction rates observed in the clinical trials of a drug cannot be directly compared to rates in the clinical trials of another drug and may not reflect the rates observed in practice.

Pioglitazone

Over 8,500 patients with type 2 diabetes have been treated with pioglitazone in randomized, double-blind, controlled clinical trials, including 2,605 patients with type 2 diabetes and macrovascular disease treated with pioglitazone from the PROactive clinical trial. In these trials, over 6,000 patients have been treated with pioglitazone for 6 months or longer, over 4,500 patients have been treated with pioglitazone for one year or longer, and over 3,000 patients have been treated with pioglitazone for at least 2 years.

In six pooled 16- to 26-week placebo-controlled monotherapy and 16- to 24-week add-on combination therapy trials, the incidence of withdrawals due to adverse events was 4.5% for patients treated with pioglitazone and 5.8% for comparator-treated patients.

The most common adverse events leading to withdrawal were related to inadequate glycemic control, although the incidence of these events was lower (1.5%) with pioglitazone than with placebo (3%).

In the PROactive trial, the incidence of withdrawals due to adverse events was 9% for patients treated with pioglitazone and 7.7% for placebo-treated patients. Congestive heart failure was the most common serious adverse event leading to withdrawal occurring in 1.3% of patients treated with pioglitazone and 0.6% of patients treated with placebo.

Common Adverse Events: 16- to 26-Week Monotherapy Trials

A summary of the incidence and type of common adverse events reported in three pooled 16- to 26-week placebo-controlled monotherapy trials of pioglitazone is provided in Table 1. Terms that are reported represent those that occurred at an incidence of >5% and more commonly in patients treated with pioglitazone than in patients who received placebo. None of these adverse events were related to the pioglitazone dose.

Table 1. Three Pooled 16- to 26-Week Placebo-Controlled Clinical Trials of Pioglitazone Monotherapy: Adverse Events Reported at an Incidence >5% and More Commonly in Patients Treated with Pioglitazone than in Patients Treated with Placebo
% of Patients
 | Placebo N=259 | Pioglitazone N=606
Upper Respiratory Tract Infection | 8.5 | 13.2
Headache | 6.9 | 9.1
Sinusitis | 4.6 | 6.3
Myalgia | 2.7 | 5.4
Pharyngitis | 0.8 | 5.1

Common Adverse Events: 16- to 24-Week Add-on Combination Therapy Trials

A summary of the overall incidence and types of common adverse events reported in trials of pioglitazone add-on to metformin is provided in Table 2. Terms that are reported represent those that occurred at an incidence of >5% and more commonly with the highest tested dose of pioglitazone.

Table 2. 16- to 24-Week Clinical Trials of Pioglitazone Add-on to Metformin
 | 16-Week Placebo-Controlled Trial Adverse Events Reported in >5% of Patients and More Commonly in Patients Treated with Pioglitazone + Metformin than in Patients Treated with Placebo + Metformin
 | % of Patients
 | Placebo + Metformin N=160 | Pioglitazone 30 mg + Metformin N=168
Edema | 2.5 | 6
Headache | 1.9 | 6
 | 24-Week Non-Controlled Double-Blind Trial Adverse Events Reported in >5% of Patients and More Commonly in Patients Treated with Pioglitazone 45 mg + Metformin than in Patients Treated with Pioglitazone 30 mg + Metformin
 | % of Patients
 | Pioglitazone 30 mg + Metformin N=411 | Pioglitazone 45 mg + Metformin N=416
Upper Respiratory Tract Infection | 12.4 | 13.5
Edema | 5.8 | 13.9
Headache | 5.4 | 5.8
Weight Increased | 2.9 | 6.7
Note: The preferred terms of edema peripheral, generalized edema, pitting edema, and fluid retention were combined to form the aggregate term of "edema."

Common Adverse Events: 24-Week Pioglitazone and Metformin Hydrochloride Clinical Trial

Table 3 summarizes the incidence and types of adverse reactions reported in a controlled, 24-week double-blind clinical trial of pioglitazone and metformin hydrochloride dosed twice daily in patients with inadequate glycemic control on diet and exercise (N=600).

- Table 3 Adverse Events (≥5% for Pioglitazone and Metformin Hydrochloride) Reported by Patients with Inadequate Glycemic Control on Diet and Exercise in a 24-Week Double-Blind Clinical Trial of Pioglitazone and Metformin Hydrochloride Administered Twice Daily
% of Patients
 | Pioglitazone and Metformin Hydrochloride 15/850 mg Twice Daily N=201 | Pioglitazone 15 mg Twice Daily N=190 | Metformin 850 mg Twice Daily N=209
Diarrhea | 9 | 2.6 | 15.3
Headache | 5.5 | 2.6 | 4.8

In this 24-week trial, abdominal pain was reported in 2% of patients in the pioglitazone and metformin hydrochloride group, 1.6% in the pioglitazone monotherapy group and 3.3% in the metformin monotherapy group.

Common Adverse Events: PROactive Trial

A summary of the overall incidence and types of common adverse events reported in the PROactive trial is provided in Table 4. Terms that are reported represent those that occurred at an incidence of >5% and more commonly in patients treated with pioglitazone than in patients who received placebo.

Table 4. PROactive Trial: Incidence and Types of Adverse Events Reported in >5% of Patients Treated with Pioglitazone and More Commonly than Placebo
 | % of Patients
 | Placebo N=2633 | Pioglitazone N=2605
Hypoglycemia | 18.8 | 27.3
Edema | 15.3 | 26.7
Cardiac Failure | 6.1 | 8.1
Pain in Extremity | 5.7 | 6.4
Back Pain | 5.1 | 5.5
Chest Pain | 5 | 5.1
Mean duration of patient follow-up was 34.5 months.

Congestive Heart Failure

A summary of the incidence of adverse events related to congestive heart failure is provided in Table 5 for the 16- to 24-week add-on to metformin trials. None of the events were fatal.

Table 5. Treatment-Emergent Adverse Events of Congestive Heart Failure (CHF) Patients Treated with Pioglitazone or Placebo Added on to Metformin
 | Number (%) of Patients
 | Placebo-Controlled Trial (16 weeks) |  | Non-Controlled Double-Blind Trial (24 weeks)
 | Placebo + Metformin N=160 | Pioglitazone 30 mg + Metformin N=168 | Pioglitazone 30 mg + Metformin N=411 | Pioglitazone 45 mg + Metformin N=416
At least one congestive heart failure event | 0 | 1 (0.6%) | 0 | 1 (0.2%)
Hospitalized | 0 | 1 (0.6%) | 0 | 1 (0.2%)

Table 6. Treatment-Emergent Adverse Events of Congestive Heart Failure (CHF)
Patients Treated with Pioglitazone or Placebo Added on to a Sulfonylurea
 | Number (%) of Patients
 | Placebo-Controlled Trial (16 weeks) |  |  | Non-Controlled Double-Blind Trial (24 weeks)
 | Placebo + Sulfonylurea N=187 | Pioglitazone 15 mg + Sulfonylurea N=184 | Pioglitazone 30 mg + Sulfonylurea N=189 | Pioglitazone 30 mg + Sulfonylurea N=351 | Pioglitazone 45 mg + Sulfonylurea N=351
At least one congestive heart failure event | 2 (1.1%) | 0 | 0 | 1 (0.3%) | 6 (1.7%)
Hospitalized | 2 (1.1%) | 0 | 0 | 0 | 2 (0.6%)
Patients Treated with Pioglitazone or Placebo Added on to Insulin
 | Number (%) of Patients
 | Placebo-Controlled Trial (16 weeks) |  |  | Non-Controlled Double-Blind Trial (24 weeks)
 | Placebo + Insulin N=187 | Pioglitazone 15 mg + Insulin N=191 | Pioglitazone 30 mg + Insulin N=188 | Pioglitazone 30 mg + Insulin N=345 | Pioglitazone 45 mg + Insulin N=345
At least one congestive heart failure event | 0 | 2 (1%) | 2 (1.1%) | 3 (0.9%) | 5 (1.4%)
Hospitalized | 0 | 2 (1%) | 1 (0.5%) | 1 (0.3%) | 3 (0.9%)
Patients Treated with Pioglitazone or Placebo Added on to Metformin
 | Number (%) of Patients
 | Placebo-Controlled Trial (16 weeks) |  |  | Non-Controlled Double-Blind Trial (24 weeks)
 | Placebo + Metformin N=160 | Pioglitazone 30 mg + Metformin N=168 |  | Pioglitazone 30 mg + Metformin N=411 | Pioglitazone 45 mg + Metformin N=416
At least one congestive heart failure event | 0 | 1 (0.6%) |  | 0 | 1 (0.2%)
Hospitalized | 0 | 1 (0.6%) |  | 0 | 1 (0.2%)

Table 7. Treatment-Emergent Adverse Events of Congestive Heart Failure (CHF) in Patients with NYHA Class II or III Congestive Heart Failure Treated with Pioglitazone or Glyburide
 | Number (%) of Subjects
 | Pioglitazone N=262 | Glyburide N=256
Death due to cardiovascular causes (adjudicated) | 5 (1.9%) | 6 (2.3%)
Overnight hospitalization for worsening CHF (adjudicated) | 26 (9.9%) | 12 (4.7%)
Emergency room visit for CHF (adjudicated) | 4 (1.5%) | 3 (1.2%)
Patients experiencing CHF progression during study | 35 (13.4%) | 21 (8.2%)

Congestive heart failure events leading to hospitalization that occurred during the PROactive trial are summarized in Table 8.

Table 8. Treatment-Emergent Adverse Events of Congestive Heart Failure (CHF) in PROactive Trial
 | Number (%) of Patients
 | Placebo N=2633 | Pioglitazone N=2605
At least one hospitalized congestive heart failure event | 108 (4.1%) | 149 (5.7%)
Fatal | 22 (0.8%) | 25 (1%)
Hospitalized, nonfatal | 86 (3.3%) | 124 (4.7%)

Cardiovascular Safety

In the PROactive trial, 5,238 patients with type 2 diabetes and a history of macrovascular disease were randomized to pioglitazone (N=2,605), force-titrated up to 45 mg daily or placebo (N=2,633) in addition to standard of care. Almost all patients (95%) were receiving cardiovascular medications (beta blockers, ACE inhibitors, angiotensin II receptor blockers, calcium channel blockers, nitrates, diuretics, aspirin, statins, and fibrates). At baseline, patients had a mean age of 62 years, mean duration of diabetes of 9.5 years, and mean HbA1c of 8.1%. Mean duration of follow-up was 34.5 months.

The primary objective of this trial was to examine the effect of pioglitazone on mortality and macrovascular morbidity in patients with type 2 diabetes mellitus who were at high risk for macrovascular events. The primary efficacy variable was the time to the first occurrence of any event in a cardiovascular composite endpoint that included all-cause mortality, non-fatal myocardial infarction (MI) including silent MI, stroke, acute coronary syndrome, cardiac intervention including coronary artery bypass grafting or percutaneous intervention, major leg amputation above the ankle, and bypass surgery or revascularization in the leg. A total of 514 (19.7%) patients treated with pioglitazone and 572 (21.7%) placebo-treated patients experienced at least one event from the primary composite endpoint (HR 0.90; 95% CI: 0.80, 1.02; p=0.10).

Although there was no statistically significant difference between pioglitazone and placebo for the 3-year incidence of a first event within this composite, there was no increase in mortality or in total macrovascular events with pioglitazone. The number of first occurrences and total individual events contributing to the primary composite endpoint is shown in Table 9.

Table 9. PROactive Trial: Number of First and Total Events for Each Component Within the Cardiovascular Composite Endpoint
Cardiovascular Events | Placebo n=2633 |  | Pioglitazone N=2605
Cardiovascular Events | First Events n (%) | Total Events n | First; Events n (%) | Total Events n
Any event | 572 (21.7) | 900 | 514 (19.7) | 803
All-cause mortality | 122 (4.6) | 186 | 110 (4.2) | 177
Nonfatal myocardial infarction (MI) | 118 (4.5) | 157 | 105 (4) | 131
Stroke | 96 (3.6) | 119 | 76 (2.9) | 92
Acute coronary syndrome | 63 (2.4) | 78 | 42 (1.6) | 65
Cardiac intervention (CABG/PCI) | 101 (3.8) | 240 | 101 (3.9) | 195
Major leg amputation | 15 (0.6) | 28 | 9 (0.3) | 28
Leg revascularization | 57 (2.2) | 92 | 71 (2.7) | 115
CABG = coronary artery bypass grafting; PCI = percutaneous intervention

Weight Gain

Dose-related weight gain occurs when pioglitazone is used alone or in combination with other antidiabetic medications. The mechanism of weight gain is unclear but probably involves a combination of fluid retention and fat accumulation.

Tables 10, 11, and 12 summarize the changes in body weight with pioglitazone and placebo in the 16- to 26-week randomized, double-blind monotherapy and 16- to 24-week combination add-on therapy trials, the PROactive trial., and the 24-week pioglitazone and metformin hydrochloride trial.

Table 10. Weight Changes (kg) from Baseline During Randomized, Double-Blind Clinical Trials
 |  | Control Group (Placebo) | Pioglitazone 15 mg | Pioglitazone 30 mg | Pioglitazone 45 mg
 |  | Median (25th, 75th percentile) | Median (25th, 75th percentile) | Median (25th, 75th percentile) | Median (25th, 75th percentile)
Monotherapy (16 to 26 weeks) |  | -1.4 (-2.7, 0) N=256 | 0.9 (-0.5, 3.4) N=79 | 1 (-0.9, 3.4) N=188 | 2.6 (0.2, 5.4) N=79
Combination Therapy (16 to 24 weeks) | Sulfonylurea | -0.5 (-1.8, 0.7) N=187 | 2 (0.2, 3.2) N=183 | 3.1 (1.1, 5.4) N=528 | 4.1 (1.8, 7.3) N=333
Combination Therapy (16 to 24 weeks) | Metformin | -1.4 (-3.2, 0.3) N=160 | N/A | 0.9 (-1.3, 3.2) N=567 | 1.8 (-0.9, 5) N=407
Combination Therapy (16 to 24 weeks) | Insulin | 0.2 (-1.4, 1.4) N=182 | 2.3 (0.5, 4.3) N=190 | 3.3 (0.9, 6.3) N=522 | 4.1 (1.4, 6.8) N=338

Table 11. Median Change in Body Weight in Patients Treated with Pioglitazone Versus Patients Treated with Placebo During the Double-Blind Treatment Period in the PROactive Trial
 | Placebo | Pioglitazone
 | Median (25th, 75th percentile) | Median (25th, 75th percentile)
Change from baseline to final visit (kg) | -0.5 (-3.3, 2) N=2581 | +3.6 (0, 7.5) N=2560
Note: Median exposure for both pioglitazone and placebo was 2.7 years.

- Table 12 Weight Changes (kg) from Baseline During Double-Blind Clinical Trial with Pioglitazone and Metformin Hydrochloride in Patients with Inadequate Glycemic Control on Diet and Exercise
 | Pioglitazone and Metformin Hydrochloride 15/850 mg Twice Daily | Pioglitazone 15 mg Twice Daily | Metformin 850 mg Twice Daily
 | Median (25th, 75th percentile) | Median (25th, 75th percentile) | Median (25th, 75th percentile)
Change from baseline to final visit (kg) | 1 (-1, 3) N=198 | 1.35 (-0.7, 4.1) N=178 | -1 (-2.6, 0.4) N=203

Note: Trial duration of 24 weeks.

Edema

Edema induced from taking pioglitazone is reversible when pioglitazone is discontinued. The edema usually does not require hospitalization unless there is coexisting congestive heart failure.

In the 24-week pioglitazone and metformin hydrochloride trial, edema was reported in 3.0% of patients in the pioglitazone and metformin hydrochloride group, 4.2% in the pioglitazone monotherapy group, and 1.4% in the metformin monotherapy group.

A summary of the frequency and types of edema adverse events occurring in clinical investigations of pioglitazone is provided in Table 13.

Table 13. Adverse Events of Edema in Patients Treated with Pioglitazone
 |  | Number (%) of Patients
 |  | Placebo |  | Pioglitazone 15 mg | Pioglitazone 30 mg | Pioglitazone 45 mg
Monotherapy (16 to 26 weeks) |  | 3 (1.2%) N=259 |  | 2 (2.5%) N= 81 | 13 (4.7%) N= 275 | 11 (6.5%) N=169
Combined Therapy (16 to 24 weeks) | Sulfonylurea | 4 (2.1%) N=187 |  | 3 (1.6%) N=184 | 61 (11.3%) N=540 | 81 (23.1%) N=351
Combined Therapy (16 to 24 weeks) | Metformin | 4 (2.5%) N=160 |  | N/A | 34 (5.9%) N=579 | 58 (13.9%) N=416
Combined Therapy (16 to 24 weeks) | Insulin | 13 (7%) N=187 |  | 24 (12.6%) N=191 | 109 (20.5%) N=533 | 90 (26.1%) N=345
Note: The preferred terms of edema peripheral, generalized edema, pitting edema, and fluid retention were combined to form the aggregate term of "edema."
Table 14. Adverse Events of Edema in Patients in the PROactive Trial
Number (%) of Patients
Placebo N=2633 |  |  | Pioglitazone N=2605
419 (15.9%) |  |  | 712 (27.3%)
Note: The preferred terms of edema peripheral, generalized edema, pitting edema, and fluid retention were combined to form the aggregate term of "edema."

Hepatic Effects

There has been no evidence of pioglitazone-induced hepatotoxicity in the pioglitazone controlled clinical trial database to date. One randomized, double-blind, 3-year trial comparing pioglitazone to glyburide as add-on to metformin and insulin therapy was specifically designed to evaluate the incidence of serum ALT elevation to greater than three times the upper limit of the reference range, measured every 8 weeks for the first 48 weeks of the trial then every 12 weeks thereafter. A total of 3/1,051 (0.3%) patients treated with pioglitazone and 9/1,046 (0.9%) patients treated with glyburide developed ALT values greater than three times the upper limit of the reference range. None of the patients treated with pioglitazone in the pioglitazone controlled clinical trial database to date have had a serum ALT greater than three times the upper limit of the reference range and a corresponding total bilirubin greater than two times the upper limit of the reference range, a combination predictive of the potential for severe drug-induced liver injury.

Hypoglycemia

In the pioglitazone clinical trials, adverse events of hypoglycemia were reported based on clinical judgment of the investigators and did not require confirmation with fingerstick glucose testing.

In the 16-week add-on to sulfonylurea trial, the incidence of reported hypoglycemia was 3.7% with pioglitazone 30 mg and 0.5% with placebo. In the 16-week add-on to insulin trial, the incidence of reported hypoglycemia was 7.9% with pioglitazone 15 mg, 15.4% with pioglitazone 30 mg, and 4.8% with placebo.

The incidence of reported hypoglycemia was higher with pioglitazone 45 mg compared to pioglitazone 30 mg in both the 24-week add-on to sulfonylurea trial (15.7% versus 13.4%) and in the 24-week add-on to insulin trial (47.8% versus 43.5%).

Three patients in these four trials were hospitalized due to hypoglycemia. All three patients were receiving pioglitazone 30 mg (0.9%) in the 24-week add-on to insulin trial. An additional 14 patients reported severe hypoglycemia (defined as causing considerable interference with patient’s usual activities) that did not require hospitalization. These patients were receiving pioglitazone 45 mg in combination with sulfonylurea (n=2) or pioglitazone 30 mg or 45 mg in combination with insulin (n=12).

Urinary Bladder Tumors

Tumors were observed in the urinary bladder of male rats in the two-year carcinogenicity study [see NONCLINICAL TOXICOLOGY (13.1)]. In two 3-year trials in which pioglitazone was compared to placebo or glyburide, there were 16/3,656 (0.44%) reports of bladder cancer in patients taking pioglitazone compared to 5/3,679 (0.14%) in patients not taking pioglitazone. After excluding patients in whom exposure to study drug was less than one year at the time of diagnosis of bladder cancer, there were six (0.16%) cases on pioglitazone and two (0.05%) cases on placebo. There are too few events of bladder cancer to establish causality.

Metformin hydrochloride

In a double-blind clinical study of metformin in patients with type 2 diabetes, a total of 141 patients received metformin therapy (up to 2550 mg per day) and 145 patients received placebo. Adverse reactions reported in greater than 5% of the metformin patients, and that were more common in metformin than placebo-treated patients, are listed in Table 15. In this trial, diarrhea led to discontinuation of study medication in 6% of patients treated with metformin.

Table 15. Most Common Adverse Reactions (>5%) in a Placebo-Controlled Clinical Study of Metformin Monotherapy [Reactions that were more common in metformin than placebo-treated patients.]
Adverse Reaction | Metformin Monotherapy (n=141) | Placebo (n=145)
Adverse Reaction | % of Patients
Diarrhea | 53.2 | 11.7
Nausea/Vomiting | 25.5 | 8.3
Flatulence | 12.1 | 5.5
Asthenia | 9.2 | 5.5
Indigestion | 7.1 | 4.1
Abdominal Discomfort | 6.4 | 4.8
Headache | 5.7 | 4.8

Laboratory Abnormalities

Hematologic Effects

Pioglitazone may cause decreases in hemoglobin and hematocrit. In placebo-controlled monotherapy trials, mean hemoglobin values declined by 2% to 4% in patients treated with pioglitazone compared with a mean change in hemoglobin of -1% to +1% in placebo-treated patients. These changes primarily occurred within the first 4 to 12 weeks of therapy and remained relatively constant thereafter. These changes may be related to increased plasma volume associated with pioglitazone therapy and are not likely to be associated with any clinically significant hematologic effects.

Vitamin B12 Concentrations

Metformin may lower serum vitamin B12 concentrations. Measurement of hematologic parameters on an annual basis is advised in patients on pioglitazone and metformin hydrochloride and any apparent abnormalities should be appropriately investigated and managed [see WARNINGS AND PRECAUTIONS (5.14)].

Creatine Phosphokinase

During protocol-specified measurement of serum creatine phosphokinase (CPK) in pioglitazone clinical trials, an isolated elevation in CPK to greater than 10 times the upper limit of the reference range was noted in 9 (0.2%) patients treated with pioglitazone (values of 2150 to 11400 IU/L) and in no comparator-treated patients. Six of these nine patients continued to receive pioglitazone, two patients were noted to have the CPK elevation on the last day of dosing, and one patient discontinued pioglitazone due to the elevation. These elevations resolved without any apparent clinical sequelae. The relationship of these events to pioglitazone therapy is unknown.

6.2 Postmarketing Experience

Pioglitazone

The following adverse reactions have been identified during post-approval use of pioglitazone. Because these reactions are reported voluntarily from a population of uncertain size, it is generally not possible to reliably estimate their frequency or establish a causal relationship to drug exposure.

- •New onset or worsening diabetic macular edema with decreased visual acuity [see WARNINGS AND PRECAUTIONS (5.8)].
- •Fatal and nonfatal hepatic failure [see WARNINGS AND PRECAUTIONS (5.5)].

Postmarketing reports of congestive heart failure have been reported in patients treated with pioglitazone, both with and without previously known heart disease and both with and without concomitant insulin administration.

In postmarketing experience, there have been reports of unusually rapid increases in weight and increases in excess of that generally observed in clinical trials. Patients who experience such increases should be assessed for fluid accumulation and volume-related events such as excessive edema and congestive heart failure [see Boxed Warning and WARNINGS AND PRECAUTIONS (5.1)].

7 DRUG INTERACTIONS

7.1 Strong CYP2C8 Inhibitors

An inhibitor of CYP2C8 (e.g., gemfibrozil) significantly increases the exposure (area under the serum concentration-time curve or AUC) and half-life (t½) of pioglitazone. Therefore, the maximum recommended dose of pioglitazone is 15 mg daily if used in combination with gemfibrozil or other strong CYP2C8 inhibitors [see DOSAGE AND ADMINISTRATION (2.3) and CLINICAL PHARMACOLOGY (12.3)].

7.2 CYP2C8 Inducers

An inducer of CYP2C8 (e.g., rifampin) may significantly decrease the exposure (AUC) of pioglitazone. Therefore, if an inducer of CYP2C8 is started or stopped during treatment with pioglitazone, changes in diabetes treatment may be needed based on clinical response without exceeding the maximum recommended daily dose of 45 mg for pioglitazone [see CLINICAL PHARMACOLOGY (12.3)].

7.3 Carbonic Anhydrase Inhibitors

Topiramate or other carbonic anhydrase inhibitors (e.g., zonisamide, acetazolamide or dichlorphenamide) frequently decrease serum bicarbonate and induce non-anion gap, hyperchloremic metabolic acidosis. Concomitant use of these drugs may induce metabolic acidosis. Use these drugs with caution in patients treated with metformin, as the risk of lactic acidosis may increase.

7.4 Cationic Drugs

Cationic drugs (e.g., amiloride, digoxin, morphine, procainamide, quinidine, quinine, ranitidine, triamterene, trimethoprim, or vancomycin) that are eliminated by renal tubular secretion theoretically have the potential for interaction with metformin by competing for common renal tubular transport systems. Although such interactions remain theoretical (except for cimetidine), careful patient monitoring and dose adjustment of pioglitazone and metformin hydrochloride and/or the interfering drug is recommended in patients who are taking cationic medications that are excreted via the proximal renal tubular secretory system [see CLINICAL PHARMACOLOGY (12.3)].

7.5 Drugs Affecting Glycemic Control

Certain drugs tend to produce hyperglycemia and may lead to loss of glycemic control. These drugs include the thiazides and other diuretics, corticosteroids, phenothiazines, thyroid products, estrogens, oral contraceptives, phenytoin, nicotinic acid, sympathomimetics, calcium channel blockers, and isoniazid. When such drugs are administered to a patient receiving pioglitazone and metformin hydrochloride, the patient should be closely observed for loss of blood glucose control. When such drugs are withdrawn from a patient receiving pioglitazone and metformin hydrochloride, the patient should be observed closely for hypoglycemia.

8 USE IN SPECIFIC POPULATIONS

8.1 Pregnancy

Pregnancy Category C

There are no adequate and well-controlled studies of pioglitazone and metformin hydrochloride or its individual components in pregnant women. Animal studies using pioglitazone show increased rates of post-implantation loss, delayed development, reduced fetal weights, and delayed parturition at doses 10 to 40 times the maximum recommended human dose. Pioglitazone and metformin hydrochloride should be used during pregnancy only if the potential benefit justifies the potential risk to the fetus.

Pioglitazone

Clinical Considerations

Abnormal blood glucose concentrations during pregnancy are associated with a higher incidence of congenital anomalies, as well as increased neonatal morbidity and mortality. Most experts recommend the use of insulin during pregnancy to maintain blood glucose concentrations as close to normal as possible for patients with diabetes.

Animal Data

In animal reproductive studies, pregnant rats and rabbits received pioglitazone at doses up to approximately 17 (rat) and 40 (rabbit) times the maximum recommended human oral dose (MRHD) based on body surface area (mg/m^2); no teratogenicity was observed. Increases in embryotoxicity (increased postimplantation losses, delayed development, reduced fetal weights, and delayed parturition) occurred in rats that received oral doses approximately 10 or more times the MRHD (mg/m^2 basis). No functional or behavioral toxicity was observed in rat offspring. When pregnant rats received pioglitazone during late gestation and lactation, delayed postnatal development, attributed to decreased body weight, occurred in rat offspring at oral maternal doses approximately 2 or more times the MRHD (mg/m^2 basis). In rabbits, embryotoxicity occurred at oral doses approximately 40 times the MRHD (mg/m^2 basis).

Metformin hydrochloride

Metformin was not teratogenic in rats and rabbits at doses up to 600 mg/kg/day. This represents an exposure of about two and six times a human daily dose of 2000 mg based on body surface area comparisons for rats and rabbits, respectively. However, because animal reproduction studies are not always predictive of human response, metformin should not be used during pregnancy unless clearly needed.

8.2 Labor and Delivery

The effect of pioglitazone and metformin hydrochloride on labor and delivery in humans is not known.

8.3 Nursing Mothers

No studies have been conducted with the combined components of pioglitazone and metformin hydrochloride. In studies performed with the individual components, both pioglitazone and metformin are secreted in the milk of lactating rats. It is not known whether pioglitazone and/or metformin are secreted in human milk. Because many drugs are excreted in human milk, and because of the potential for pioglitazone and metformin hydrochloride to cause serious adverse reactions in nursing infants, a decision should be made to discontinue nursing or discontinue pioglitazone and metformin hydrochloride, taking into account the importance of pioglitazone and metformin hydrochloride to the mother.

8.4 Pediatric Use

Safety and effectiveness of pioglitazone and metformin hydrochloride in pediatric patients have not been established.

Pioglitazone and metformin hydrochloride is not recommended for use in pediatric patients based on adverse effects observed in adults, including fluid retention and congestive heart failure, fractures, and urinary bladder tumors [see WARNINGS AND PRECAUTIONS (5.1, 5.3, 5.6, 5.7)].

8.5 Geriatric Use

Pioglitazone

A total of 92 patients (15.2%) treated with pioglitazone in the three pooled 16- to 26-week double-blind, placebo-controlled, monotherapy trials were ≥65 years old and 2 patients (0.3%) were ≥75 years old. In the two pooled 16- to 24-week add-on to sulfonylurea trials, 201 patients (18.7%) treated with pioglitazone were ≥65 years old and 19 (1.8%) were ≥75 years old. In the two pooled 16- to 24-week add-on to metformin trials, 155 patients (15.5%) treated with pioglitazone were ≥65 years old and 19 (1.9%) were ≥75 years old. In the two pooled 16- to 24-week add-on to insulin trials, 272 patients (25.4%) treated with pioglitazone were ≥65 years old and 22 (2.1%) were ≥75 years old.

In PROactive Trial, 1,068 patients (41%) treated with pioglitazone were ≥65 years old and 42 (1.6%) were ≥75 years old.

In pharmacokinetic studies with pioglitazone, no significant differences were observed in pharmacokinetic parameters between elderly and younger patients [see CLINICAL PHARMACOLOGY (12.3)].

Although clinical experiences have not identified differences in effectiveness and safety between the elderly (≥65 years) and younger patients, these conclusions are limited by small sample sizes for patients ≥75 years old.

Metformin hydrochloride

Controlled clinical studies of metformin did not include sufficient numbers of elderly patients to determine whether they respond differently from younger patients, although other reported clinical experience has not identified differences in responses between the elderly and young patients. Metformin is known to be substantially excreted by the kidney and because the risk of serious adverse reactions to the drug is greater in patients with impaired renal function, pioglitazone and metformin hydrochloride should only be used in patients with normal renal function [see CONTRAINDICATIONS (4), WARNINGS AND PRECAUTIONS (5.2), and CLINICAL PHARMACOLOGY (12.3)]. Because aging is associated with reduced renal function, pioglitazone and metformin hydrochloride should be used with caution as age increases. Care should be taken in dose selection and should be based on careful and regular monitoring of renal function. Generally, elderly patients should not be titrated to the maximum dose of pioglitazone and metformin hydrochloride [see WARNINGS AND PRECAUTIONS (5.2) and DOSAGE AND ADMINISTRATION (2)].

10 OVERDOSAGE

Pioglitazone

During controlled clinical trials, one case of overdose with pioglitazone was reported. A male patient took 120 mg per day for four days, then 180 mg per day for seven days. The patient denied any clinical symptoms during this period.

In the event of overdosage, appropriate supportive treatment should be initiated according to the patient's clinical signs and symptoms.

Metformin hydrochloride

Overdose of metformin hydrochloride has occurred, including ingestion of amounts greater than 50 grams. Hypoglycemia was reported in approximately 10% of cases, but no causal association with metformin hydrochloride has been established. Lactic acidosis has been reported in approximately 32% of metformin overdose cases [see WARNINGS AND PRECAUTIONS (5.2)]. Metformin is dialyzable with a clearance of up to 170 mL/min under good hemodynamic conditions. Therefore, hemodialysis may be useful for removal of accumulated metformin from patients in whom metformin overdosage is suspected.

11 DESCRIPTION

Pioglitazone and metformin hydrochloride tablets, USP are a thiazolidinediones and biguanide combination product that contains two oral antidiabetic medications: pioglitazone and metformin hydrochloride.

Pioglitazone [(±)-5-[[4-[2-(5-ethyl-2-pyridinyl) ethoxy]phenyl]methyl]-2,4-] thiazolidinedione monohydrochloride contains one asymmetric carbon, and the compound is synthesized and used as the racemic mixture. The two enantiomers of pioglitazone interconvert in vivo. No differences were found in the pharmacologic activity between the two enantiomers. The structural formula is as shown:

Pioglitazone hydrochloride is an odorless white to off white crystalline powder that has a molecular formula of C19H20N2O3S•HCl and a molecular weight of 392.91. It is soluble in N,N-dimethylformamide, slightly soluble in anhydrous ethanol, very slightly soluble in acetone and acetonitrile, practically insoluble in water, and insoluble in ether.

Metformin hydrochloride (N,N-dimethylimidodicarbonimidic diamide hydrochloride) is a white to almost white crystalline powder with a molecular formula of C4H11N5•HCl and a molecular weight of 165.62. Metformin hydrochloride is freely soluble in water and is practically insoluble in acetone, ether, and chloroform. The pKa of metformin is 12.4. The pH of a 1% aqueous solution of metformin hydrochloride is 6.68. The structural formula is as shown:

Pioglitazone and metformin hydrochloride tablets, USP are available for oral administration containing 15 mg pioglitazone (as the base) with 500 mg metformin hydrochloride (15 mg/500 mg) or 15 mg pioglitazone (as the base) with 850 mg metformin hydrochloride (15 mg/850 mg) formulated with the following inactive ingredients: croscarmellose sodium, hydroxypropylcellulose, hypromellose, magnesium stearate, microcrystalline cellulose, polyethylene glycol, povidone, talc, and titanium dioxide.

12 CLINICAL PHARMACOLOGY

12.1 Mechanism of Action

Pioglitazone and metformin hydrochloride combines two antidiabetic medications with different mechanisms of action to improve glycemic control in adults with type 2 diabetes: pioglitazone, a thiazolidinedione, and metformin hydrochloride, a biguanide. Thiazolidinediones are insulin-sensitizing agents that act primarily by enhancing peripheral glucose utilization, whereas biguanides act primarily by decreasing endogenous hepatic glucose production.

Pioglitazone

Pioglitazone is a thiazolidinedione that depends on the presence of insulin for its mechanism of action. Pioglitazone decreases insulin resistance in the periphery and in the liver resulting in increased insulin-dependent glucose disposal and decreased hepatic glucose output. Pioglitazone is not an insulin secretagogue. Pioglitazone is an agonist for peroxisome proliferator-activated receptor-gamma (PPARγ). PPAR receptors are found in tissues important for insulin action such as adipose tissue, skeletal muscle, and liver. Activation of PPARγ nuclear receptors modulates the transcription of a number of insulin responsive genes involved in the control of glucose and lipid metabolism.

In animal models of diabetes, pioglitazone reduces the hyperglycemia, hyperinsulinemia, and hypertriglyceridemia characteristic of insulin-resistant states such as type 2 diabetes. The metabolic changes produced by pioglitazone result in increased responsiveness of insulin-dependent tissues and are observed in numerous animal models of insulin resistance.

Because pioglitazone enhances the effects of circulating insulin (by decreasing insulin resistance), it does not lower blood glucose in animal models that lack endogenous insulin.

Metformin hydrochloride

Metformin hydrochloride improves glucose tolerance in patients with type 2 diabetes, lowering both basal and postprandial plasma glucose. Metformin decreases hepatic glucose production, decreases intestinal absorption of glucose, and improves insulin sensitivity by increasing peripheral glucose uptake and utilization. Metformin does not produce hypoglycemia in either patients with type 2 diabetes or healthy subjects [except in specific circumstances, [seeWARNINGS AND PRECAUTIONS (5.4)] and does not cause hyperinsulinemia. With metformin therapy, insulin secretion remains unchanged while fasting insulin levels and day-long plasma insulin response may actually decrease.

12.2 Pharmacodynamics

Pioglitazone

Clinical studies demonstrate that pioglitazone improves insulin sensitivity in insulin-resistant patients. Pioglitazone enhances cellular responsiveness to insulin, increases insulin-dependent glucose disposal and improves hepatic sensitivity to insulin. In patients with type 2 diabetes, the decreased insulin resistance produced by pioglitazone results in lower plasma glucose concentrations, lower plasma insulin concentrations, and lower HbA1c values. In controlled clinical trials, pioglitazone had an additive effect on glycemic control when used in combination with a sulfonylurea, metformin, or insulin [see CLINICAL STUDIES (14)].

Patients with lipid abnormalities were included in clinical trials with pioglitazone. Overall, patients treated with pioglitazone had mean decreases in serum triglycerides, mean increases in HDL cholesterol, and no consistent mean changes in LDL and total cholesterol. There is no conclusive evidence of macrovascular benefit with pioglitazone or any other antidiabetic medication [see WARNINGS AND PRECAUTIONS (5.15) and ADVERSE REACTIONS (6.1)].

In a 26-week, placebo-controlled, dose-ranging monotherapy study, mean serum triglycerides decreased in the 15-mg, 30-mg, and 45-mg pioglitazone dose groups compared to a mean increase in the placebo group. Mean HDL cholesterol increased to a greater extent in patients treated with pioglitazone than in the placebo-treated patients. There were no consistent differences for LDL and total cholesterol in patients treated with pioglitazone compared to placebo (see Table 16).

Table 16. Lipids in a 26-Week Placebo-Controlled Monotherapy Dose-Ranging Study
 | Placebo | Pioglitazone 15 mg Once Daily | Pioglitazone 30 mg Once Daily | Pioglitazone 45 mg Once Daily
Triglycerides (mg/dL) | N=79 | N=79 | N=84 | N=77
Baseline (mean) | 263 | 284 | 261 | 260
Percent change from baseline (adjusted mean [Adjusted for baseline, pooled center, and pooled center by treatment interaction]) | 4.8% | -9% [p <0.05 versus placebo] | -9.6% | -9.3%
HDL Cholesterol (mg/dL) | N=79 | N=79 | N=83 | N=77
Baseline (mean) | 42 | 40 | 41 | 41
Percent change from baseline (adjusted mean) | 8.1% | 14.1% | 12.2% | 19.1%
LDL Cholesterol (mg/dL) | N=65 | N=63 | N=74 | N=62
Baseline (mean) | 139 | 132 | 136 | 127
Percent change from baseline (adjusted mean) | 4.8% | 7.2% | 5.2% | 6%
Total Cholesterol (mg/dL) | N=79 | N=79 | N=84 | N=77
Baseline (mean) | 225 | 220 | 223 | 214
Percent change from baseline (adjusted mean) | 4.4% | 4.6% | 3.3% | 6.4%

In the two other monotherapy studies (16 weeks and 24 weeks) and in combination therapy studies with metformin (16 weeks and 24 weeks), the results were generally consistent with the data above.

12.3 Pharmacokinetics

Absorption

Pioglitazone and Metformin Hydrochloride

In bioequivalence studies of pioglitazone and metformin hydrochloride 15 mg/500 mg and 15 mg/850 mg, the area under the curve (AUC) and maximum concentration (Cmax) of both the pioglitazone and the metformin component following a single dose of the combination tablet were bioequivalent to pioglitazone hydrochloride 15 mg concomitantly administered with Glucophage (500 mg or 850 mg respectively) tablets under fasted conditions in healthy subjects.

Administration of pioglitazone and metformin hydrochloride 15 mg/850 mg with food resulted in no change in overall exposure of pioglitazone. With metformin there was no change in AUC; however, mean peak serum concentration of metformin was decreased by 28% when administered with food. A delayed time to peak serum concentration was observed for both components (1.9 hours for pioglitazone and 0.8 hours for metformin) under fed conditions. These changes are not likely to be clinically significant.

Pioglitazone

Following once-daily administration of pioglitazone, steady-state serum concentrations of both pioglitazone and its major active metabolites, M-III (keto derivative of pioglitazone) and M-IV (hydroxyl derivative of pioglitazone), are achieved within 7 days. At steady-state, M-III and M-IV reach serum concentrations equal to or greater than that of pioglitazone. At steady-state, in both healthy volunteers and patients with type 2 diabetes, pioglitazone comprises approximately 30% to 50% of the peak total pioglitazone serum concentrations (pioglitazone plus active metabolites) and 20% to 25% of the total AUC.

Cmax, AUC, and trough serum concentrations (Cmin) for pioglitazone and M-III and M-IV, increased proportionally with administered doses of 15 mg and 30 mg per day.

Following oral administration of pioglitazone, Tmax of pioglitazone was within 2 hours. Food delays the Tmax to 3 to 4 hours but does not alter the extent of absorption (AUC).

Metformin hydrochloride

The absolute bioavailability of a 500 mg metformin tablet given under fasting conditions is approximately 50% to 60%. Studies using single oral doses of metformin tablets of 500 mg to 1500 mg, and 850 mg to 2550 mg, indicate that there is a lack of dose proportionality with increasing doses, which is due to decreased absorption rather than an alteration in elimination. At usual clinical doses and dosing schedules of metformin, steady-state plasma concentrations of metformin are reached within 24 to 48 hours and are generally <1 mcg/mL. During controlled clinical trials, maximum metformin plasma levels did not exceed 5 mcg/mL, even at maximum doses.

Food decreases the rate and extent of metformin absorption, as shown by a 40% lower mean Cmax, a 25% lower AUC, and a 35-minute prolongation of Tmax following administration of a single 850 mg tablet of metformin with food, compared to the same tablet strength administered fasting. The clinical relevance of these decreases is unknown.

Distribution

Pioglitazone

The mean apparent volume of distribution (Vd/F) of pioglitazone following single-dose administration is 0.63 ± 0.41 (mean ± SD) L/kg of body weight. Pioglitazone is extensively protein bound (>99%) in human serum, principally to serum albumin. Pioglitazone also binds to other serum proteins, but with lower affinity. M-III and M-IV are also extensively bound (>98%) to serum albumin.

Metformin hydrochloride

The Vd/F of metformin following single oral doses of 850 mg immediate-release metformin averaged 654 ± 358 L. Metformin is negligibly bound to plasma proteins. Metformin partitions into erythrocytes, most likely as a function of time.

Metabolism

Pioglitazone

Pioglitazone is extensively metabolized by hydroxylation and oxidation; the metabolites also partly convert to glucuronide or sulfate conjugates. Metabolites M-III and M-IV are the major circulating active metabolites in humans.

In vitro data demonstrate that multiple CYP isoforms are involved in the metabolism of pioglitazone which include CYP2C8 and, to a lesser degree, CYP3A4 with additional contributions from a variety of other isoforms, including the mainly extrahepatic CYP1A1. In vivo study of pioglitazone in combination with gemfibrozil, a strong CYP2C8 inhibitor, showed that pioglitazone is a CYP2C8 substrate [see DOSAGE AND ADMINISTRATION (2.3) and DRUG INTERACTIONS (7.1)]. Urinary 6ß-hydroxycortisol/cortisol ratios measured in patients treated with pioglitazone showed that pioglitazone is not a strong CYP3A4 enzyme inducer.

Metformin hydrochloride

Intravenous single-dose studies in healthy subjects demonstrate that metformin is excreted unchanged in the urine and does not undergo hepatic metabolism (no metabolites have been identified in humans) nor biliary excretion.

Excretion and Elimination

Pioglitazone

Following oral administration, approximately 15% to 30% of the pioglitazone dose is recovered in the urine. Renal elimination of pioglitazone is negligible and the drug is excreted primarily as metabolites and their conjugates. It is presumed that most of the oral dose is excreted into the bile either unchanged or as metabolites and eliminated in the feces.

The mean serum half-life (t½) of pioglitazone and its metabolites (M-III and M-IV) range from 3 to 7 hours and 16 to 24 hours, respectively. Pioglitazone has an apparent clearance, CL/F, calculated to be 5 to 7 L/hr.

Metformin hydrochloride

Renal clearance is approximately 3.5 times greater than creatinine clearance (CLcr), which indicates that tubular secretion is the major route of metformin elimination. Following oral administration, approximately 90% of the absorbed drug is eliminated via the renal route within the first 24 hours, with a plasma elimination t½ of approximately 6.2 hours. In blood, the elimination t½ is approximately 17.6 hours, suggesting that the erythrocyte mass may be a compartment of distribution.

Specific Populations

Renal Impairment

Pioglitazone

The serum elimination half-life of pioglitazone, M-III and M-IV remains unchanged in patients with moderate (CLcr 30 to 50 mL/min) and severe (CLcr <30 mL/min) renal impairment when compared to subjects with normal renal function. Therefore, no dose adjustment in patients with renal impairment is required.

Metformin hydrochloride

In patients with decreased renal function (based on CLcr), the plasma and blood t1/2 of metformin is prolonged and the renal clearance is decreased in proportion to the decrease in CLcr [see CONTRAINDICATIONS (4) and WARNINGS AND PRECAUTIONS (5.2)]. Because metformin is contraindicated in patients with renal impairment, pioglitazone and metformin hydrochloride is also contraindicated in these patients.

Hepatic Impairment

Pioglitazone

Compared with healthy controls, subjects with impaired hepatic function (Child-Turcotte-Pugh Grade B/C) have an approximate 45% reduction in pioglitazone and total pioglitazone (pioglitazone, M-III, and M-IV) mean Cmax but no change in the mean AUC values. Therefore, no dose adjustment in patients with hepatic impairment is required.

There are postmarketing reports of liver failure with pioglitazone and clinical trials have generally excluded patients with serum ALT >2.5 times the upper limit of the reference range. Use pioglitazone and metformin hydrochloride with caution in patients with liver disease [see WARNINGS AND PRECAUTIONS (5.5)].

Metformin hydrochloride

No pharmacokinetic studies of metformin have been conducted in subjects with hepatic impairment. Use of metformin in patients with hepatic impairment has been associated with some cases of lactic acidosis. Pioglitazone and metformin hydrochloride is not recommended in patients with hepatic impairment [see WARNINGS AND PRECAUTIONS (5.5)].

Geriatric Patients

Pioglitazone

In healthy elderly subjects, Cmax of pioglitazone was not significantly different, but AUC values were approximately 21% higher than those achieved in younger subjects. The mean t½ of pioglitazone was also prolonged in elderly subjects (about 10 hours) as compared to younger subjects (about 7 hours). These changes were not of a magnitude that would be considered clinically relevant.

Metformin hydrochloride

Limited data from controlled pharmacokinetic studies of metformin in healthy elderly subjects suggest that total CL/F is decreased, the t½ is prolonged, and Cmax is increased, compared to healthy young subjects. From these data, it appears that the change in metformin pharmacokinetics with aging is primarily accounted for by a change in renal function.

As is true for all patients, pioglitazone and metformin hydrochloride treatment should not be initiated in geriatric patients unless measurement of CLcr demonstrates that renal function is not reduced [see WARNINGS AND PRECAUTIONS (5.2)].

Pediatrics

Pioglitazone

Safety and efficacy of pioglitazone in pediatric patients have not been established. Pioglitazone and metformin hydrochloride is not recommended for use in pediatric patients [see USE IN SPECIFIC POPULATIONS (8.4)].

Metformin hydrochloride

After administration of a single oral metformin 500 mg tablet with food, geometric mean metformin Cmax and AUC differed less than 5% between pediatric type 2 diabetic patients (12 to 16 years of age) and gender- and weight-matched healthy adults (20 to 45 years of age), and all with normal renal function.

Gender

Pioglitazone

The mean Cmax and AUC values of pioglitazone were increased 20% to 60% in women compared to men. In controlled clinical trials, HbA1c decreases from baseline were generally greater for females than for males (average mean difference in HbA1c 0.5%). Because therapy should be individualized for each patient to achieve glycemic control, no dose adjustment is recommended based on gender alone.

Metformin hydrochloride

Metformin pharmacokinetic parameters did not differ significantly between normal subjects and patients with type 2 diabetes when analyzed according to gender (males=19, females=16). Similarly, in controlled clinical studies in patients with type 2 diabetes, the antihyperglycemic effect of metformin was comparable in males and females.

Ethnicity

Pioglitazone

Pharmacokinetic data among various ethnic groups are not available.

Metformin hydrochloride

No studies of metformin pharmacokinetic parameters according to race have been performed. In controlled clinical studies of metformin in patients with type 2 diabetes, the antihyperglycemic effect was comparable in whites (n=249), blacks (n=51), and Hispanics (n=24).

Drug-Drug Interactions

Specific pharmacokinetic drug interaction studies with pioglitazone and metformin hydrochloride have not been performed, although such studies have been conducted with the individual pioglitazone and metformin components.

Pioglitazone

Table 17. Effect of Pioglitazone Coadministration on Systemic Exposure of Other Drugs
 | Coadministered Drug
Pioglitazone Dosage Regimen (mg) [Daily for 7 days unless otherwise noted] | Name and Dose Regimens | Change in AUC [% change (with/without coadministered drug and no change = 0%); symbols of ↑ and ↓ indicate the exposure increase and decrease, respectively] |  | Change in Cmax
45 mg (N = 12) | Warfarin [Pioglitazone had no clinically significant effect on prothrombin time]
45 mg (N = 12) | Daily loading then maintenance doses based PT and INR values Quick's Value = 35 ± 5% | R-Warfarin | ↓3% | R-Warfarin | ↓2%
45 mg (N = 12) | Daily loading then maintenance doses based PT and INR values Quick's Value = 35 ± 5% | S-Warfarin | ↓1% | S-Warfarin | ↑1%
45 mg (N = 12) | Digoxin
45 mg (N = 12) | 0.200 mg twice daily (loading dose) then 0.250 mg daily (maintenance dose, 7 days) | ↑15% |  | ↑17%
45 mg daily for 21 days (N = 35) | Oral Contraceptive
45 mg daily for 21 days (N = 35) | [Ethinyl Estradiol (EE) 0.035 mg plus Norethindrone (NE) 1 mg] for 21 days | EE | ↓11% | EE | ↓13%
45 mg daily for 21 days (N = 35) | [Ethinyl Estradiol (EE) 0.035 mg plus Norethindrone (NE) 1 mg] for 21 days | NE | ↑3% | NE | ↓7%
45 mg (N = 23) | Fexofenadine
45 mg (N = 23) | 60 mg twice daily for 7 days | ↑30% |  | ↑37%
45 mg (N = 14) | Glipizide
45 mg (N = 14) | 5 mg daily for 7 days | ↓3% |  | ↓8%
45 mg daily for 8 days (N = 16) | Metformin
45 mg daily for 8 days (N = 16) | 1000 mg single dose on Day 8 | ↓3% |  | ↓5%
45 mg (N = 21) | Midazolam
45 mg (N = 21) | 7.5 mg single dose on Day 15 | ↓26% |  | ↓26%
45 mg (N = 24) | Ranitidine
45 mg (N = 24) | 150 mg twice daily for 7 days | ↑1% |  | ↓1%
45 mg daily for 4 days (N = 24) | Nifedipine ER
45 mg daily for 4 days (N = 24) | 30 mg daily for 4 days | ↓13% |  | ↓17%
45 mg (N = 25) | Atorvastatin Ca
45 mg (N = 25) | 80 mg daily for 7 days | ↓14% |  | ↓23%
45 mg (N = 22) | Theophylline
45 mg (N = 22) | 400 mg twice daily for 7 days | ↑2% |  | ↑5%

Table 18. Effect of Coadministered Drugs on Pioglitazone Systemic Exposure
Coadministered Drug and Dosage Regimen | Pioglitazone
Coadministered Drug and Dosage Regimen | Dose Regimen (mg) [Daily for 7 days unless otherwise noted] | Change in AUC [Mean ratio (with/without coadministered drug and no change = 1-fold) % change (with/without coadministered drug and no change = 0%); symbols of ↑ and ↓ indicate the exposure increase and decrease, respectively] | Change in Cmax
Gemfibrozil 600 mg twice daily for 2 days (N = 12) | 15-mg single dose | ↑3.2-fold [The half-life of pioglitazone increased from 8.3 hours to 22.7 hours in the presence of gemfibrozil [see DOSAGE AND ADMINISTRATION (2.3) and DRUG INTERACTIONS (7.1)]] | ↑6%
Ketoconazole 200 mg twice daily for 7 days (N = 28) | 45 mg | ↑34% | ↑14%
Rifampin 600 mg daily for 5 days (N = 10) | 30-mg single dose | ↓54% | ↓5%
Fexofenadine 60 mg twice daily for 7 days (N = 23) | 45 mg | ↑1% | 0%
Ranitidine 150 mg twice daily for 4 days (N = 23) | 45 mg | ↓13% | ↓16%
Nifedipine ER 30 mg daily for 7 days (N = 23) | 45 mg | ↑5% | ↑4%
Atorvastatin Ca 80 mg daily for 7 days (N = 24) | 45 mg | ↓24% | ↓31%
Theophylline 400 mg twice daily for 7 days (N = 22) | 45 mg | ↓4% | ↓2%

Metformin hydrochloride

Table 19. Effect of Coadministered Drug on Plasma Metformin Systemic Exposure
Coadministered Drug | Dose of Coadministered Drug* | Dose of Metformin* | Geometric Mean Ratio (ratio with/without coadministered drug) No effect = 1.00
Coadministered Drug | Dose of Coadministered Drug* | Dose of Metformin* | AUC† | Cmax
No dosing adjustments required for the following:
Glyburide | 5 mg | 500 mg§ | 0.98‡ | 0.99‡
Furosemide | 40 mg | 850 mg | 1.09‡ | 1.22‡
Nifedipine | 10 mg | 850 mg | 1.16 | 1.21
Propranolol | 40 mg | 850 mg | 0.90 | 0.94
Ibuprofen | 400 mg | 850 mg | 1.05‡ | 1.07‡
Cationic drugs eliminated by renal tubular secretion may reduce metformin elimination: use with caution [see WARNINGS AND PRECAUTIONS (5) and DRUG INTERACTIONS (7)].
Cimetidine | 400 mg | 850 mg | 1.40 | 1.61
Carbonic anhydrase inhibitors may cause metabolic acidosis: use with caution [SEE WARNINGS AND PRECAUTIONS (5) and DRUG INTERACTIONS (7)].
Topiramate | 100 mg¶ | 500 mg¶ | 1.25¶ | 1.17

*All metformin and coadministered drugs were given as single doses

†AUC = AUC0–∞

‡Metformin hydrochloride extended-release tablets, 500 mg

§Ratio of arithmetic means

¶At steady-state with topiramate 100 mg every 12 hours and metformin 500 mg every 12 hours; AUC = AUC0-12h

Table 20. Effect of Metformin on Coadministered Drug Systemic Exposure
Coadministered Drug | Dose of Coadministered Drug* | Dose of Metformin* | Geometric Mean Ratio (ratio with/without coadministered drug) No effect = 1.00
Coadministered Drug | Dose of Coadministered Drug* | Dose of Metformin* | AUC† | Cmax
No dosing adjustments required for the following:
Glyburide | 5 mg | 500 mg§ | 0.78‡ | 0.63‡
Furosemide | 40 mg | 850 mg | 0.87‡ | 0.69‡
Nifedipine | 10 mg | 850 mg | 1.10§ | 1.08
Propranolol | 40 mg | 850 mg | 1.01§ | 0.94
Ibuprofen | 400 mg | 850 mg | 0.97¶ | 1.01¶
Cimetidine | 400 mg | 850 mg | 0.95§ | 1.01

All metformin and coadministered drugs were given as single doses

*AUC = AUC0–∞

†AUC0-24 hr reported

§Ratio of arithmetic means, p-value of difference <0.05

¶Ratio of arithmetic means

13 NONCLINICAL TOXICOLOGY

13.1 Carcinogenesis, Mutagenesis, Impairment of Fertility

Pioglitazone and Metformin Hydrochloride

No animal studies have been conducted with pioglitazone and metformin hydrochloride. The following data are based on findings in studies performed with pioglitazone or metformin individually.

Pioglitazone

A two-year carcinogenicity study was conducted in male and female rats at oral doses up to 63 mg/kg (approximately 14 times the maximum recommended human oral dose of 45 mg based on mg/m^2). Drug-induced tumors were not observed in any organ except for the urinary bladder of male rats. Benign and/or malignant transitional cell neoplasms were observed in male rats at 4 mg/kg/day and above (approximately equal to the maximum recommended human oral dose based on mg/m^2). Urinary calculi with subsequent irritation and hyperplasia were postulated as the mechanism for bladder tumors observed in male rats. A two-year mechanistic study in male rats utilizing dietary acidification to reduce calculi formation was completed in 2009. Dietary acidification decreased but did not abolish the hyperplastic changes in the bladder. The presence of calculi exacerbated the hyperplastic response to pioglitazone but was not considered the primary cause of the hyperplastic changes.

The relevance to humans of the bladder findings in the male rat cannot be excluded.

A two-year carcinogenicity study was also conducted in male and female mice at oral doses up to 100 mg/kg/day (approximately 11 times the maximum recommended human oral dose based on mg/m^2). No drug-induced tumors were observed in any organ.

Pioglitazone hydrochloride was not mutagenic in a battery of genetic toxicology studies, including the Ames bacterial assay, a mammalian cell forward gene mutation assay (CHO/HPRT and AS52/XPRT), an in vitro cytogenetics assay using CHL cells, an unscheduled DNA synthesis assay, and an in vivo micronucleus assay.

No adverse effects upon fertility were observed in male and female rats at oral doses up to 40 mg/kg pioglitazone hydrochloride daily prior to and throughout mating and gestation (approximately 9 times the maximum recommended human oral dose based on mg/m^2).

Metformin hydrochloride

Long-term carcinogenicity studies have been performed in rats (dosing duration of 104 weeks) and mice (dosing duration of 91 weeks) at doses up to and including 900 mg/kg/day and 1500 mg/kg/day, respectively. These doses are both approximately four times a human daily dose of 2000 mg of the metformin component of pioglitazone and metformin hydrochloride based on body surface area comparisons. No evidence of carcinogenicity with metformin was found in either male or female mice. Similarly, there was no tumorigenic potential observed with metformin in male rats. There was, however, an increased incidence of benign stromal uterine polyps in female rats treated with 900 mg/kg/day.

There was no evidence of mutagenic potential of metformin in the following in vitro tests: Ames test (S. typhimurium), gene mutation test (mouse lymphoma cells), or chromosomal aberrations test (human lymphocytes). Results in the in vivo mouse micronucleus test were also negative.

Fertility of male or female rats was unaffected by metformin when administered at doses as high as 600 mg/kg/day, which is approximately three times the maximum recommended human daily dose of the metformin component of pioglitazone and metformin hydrochloride based on body surface area comparisons.

13.2 Animal Toxicology and/or Pharmacology

Heart enlargement has been observed in mice (100 mg/kg), rats (4 mg/kg and above) and dogs (3 mg/kg) treated orally with pioglitazone hydrochloride (approximately 11, 1, and 2 times the maximum recommended human oral dose for mice, rats, and dogs, respectively, based on mg/m^2). In a one-year rat study, drug-related early death due to apparent heart dysfunction occurred at an oral dose of 160 mg/kg/day (approximately 35 times the maximum recommended human oral dose based on mg/m^2). Heart enlargement was seen in a 13-week study in monkeys at oral doses of 8.9 mg/kg and above (approximately 4 times the maximum recommended human oral dose based on mg/m^2), but not in a 52-week study at oral doses up to 32 mg/kg (approximately 13 times the maximum recommended human oral dose based on mg/m^2).

14 CLINICAL STUDIES

14.1 Patients Who Have Inadequate Glycemic Control with Diet and Exercise Alone

In a 24-week, randomized, double-blind clinical trial, 600 patients with type 2 diabetes mellitus inadequately controlled with diet and exercise alone (mean baseline HbA1c 8.7%) were randomized to pioglitazone and metformin hydrochloride 15/850 mg, pioglitazone 15 mg, or metformin 850 mg twice daily. Statistically significant improvements in HbA1c and fasting plasma glucose (FPG) were observed in patients treated with pioglitazone and metformin hydrochloride compared to either pioglitazone or metformin alone (see Table 21).

- Table 21 Glycemic Parameters in 24-Week Study of Pioglitazone and Metformin Hydrochloride in Patients with Type 2 Diabetes Mellitus Inadequately Controlled with Diet and Exercise
Parameter | Treatment Group
Parameter | Pioglitazone and Metformin Hydrochloride 15/850 mg Twice Daily | Pioglitazone 15 mg Twice Daily | Metformin 850 mg Twice Daily
HbA1c (%) | N=188 | N=162 | N=193
Baseline (mean) | 8.9 | 8.7 | 8.7
Change from Baseline (adjusted mean*) | -1.8 | -1 | -1
Difference between pioglitazone and metformin hydrochloride (adjusted mean*) 95% Confidence Interval |  | 0.9† (0.5, 1.2) | 0.8† (0.5, 1.2)
% of patients with HbA1c ≤7% | 64 | 47 | 39
Fasting Plasma Glucose (mg/dL) | N=196 | N=176 | N=202
Baseline (mean) | 177 | 171 | 171
Change from Baseline (adjusted mean*) | -40 | -22 | -25
Difference between pioglitazone and metformin hydrochloride (adjusted mean*) 95% Confidence Interval |  | 18† (8, 28) | 15† (6, 25)

*Adjusted for baseline

†p ≤0.05 versus pioglitazone and metformin hydrochloride

14.2 Patients Previously Treated with Metformin

The efficacy and safety of pioglitazone as add-on to metformin therapy have been established in two clinical studies. Bioequivalence of pioglitazone and metformin hydrochloride with coadministered pioglitazone and metformin was demonstrated for both pioglitazone and metformin hydrochloride tablets strengths [see CLINICAL PHARMACOLOGY (12.3)].

The two clinical trials testing pioglitazone as add-on to metformin therapy included patients with type 2 diabetes on any dose of metformin, either alone or in combination with another antidiabetic agent. All other antidiabetic agents were withdrawn at least 3 weeks prior to starting study treatment.

In the first trial, 328 patients were randomized to receive either 30 mg of pioglitazone or placebo once daily for 16 weeks in addition to their current metformin regimen. Treatment with pioglitazone as add-on to metformin produced statistically significant improvements in HbA1c and FPG at endpoint compared to placebo add-on to metformin (see Table 22).

Table 22. Glycemic Parameters in a 16-Week Placebo-Controlled, Add-on to Metformin Trial
 | Placebo + Metformin | Pioglitazone 30 mg + Metformin
Total Population
HbA1c (%) | N=153 | N=161
Baseline (mean) | 9.8 | 9.9
Change from baseline (adjusted mean*) | 0.2 | -0.6
Difference from placebo + metformin (adjusted mean*) 95% Confidence Interval |  | -0.8† (-1.2, -0.5)
Fasting Plasma Glucose (mg/dL) | N=157 | N=165
Baseline (mean) | 260 | 254
Change from baseline (adjusted mean*) | -5 | -43
Difference from placebo + metformin (adjusted mean*) 95% Confidence Interval |  | -38† (-49, -26)

*Adjusted for baseline, pooled center, and pooled center by treatment interaction

†p ≤0.05 vs. placebo + metformin

In the second trial, 827 patients were randomized to receive either 30 mg or 45 mg of pioglitazone once daily for 24 weeks in addition to their current metformin regimen. The mean reduction from baseline at Week 24 in HbA1c was 0.8% for the 30 mg dose and 1% for the 45 mg dose (see Table 23). The mean reduction from baseline at Week 24 in FPG was 38 mg/dL for the 30 mg dose and 51 mg/dL for the 45 mg dose.

Table 23. Glycemic Parameters in a 24-Week Add-on to Metformin Study
 | Pioglitazone 30 mg + Metformin | Pioglitazone 45 mg + Metformin
Total Population
HbA1c (%) | N=400 | N=398
Baseline (mean) | 9.9 | 9.8
Change from baseline (adjusted mean*) | -0.8 | -1
Difference from 30 mg daily pioglitazone + metformin (adjusted mean*) (95% CI) |  | -0.2 (-0.5, 0.1)
Fasting Plasma Glucose (mg/dL) | N=398 | N=399
Baseline (mean) | 233 | 232
Change from baseline (adjusted mean*) | -38 | -51
Difference from 30 mg daily pioglitazone + metformin (adjusted mean*) (95% CI) |  | -12† (-21, -4)
95% CI = 95% confidence interval

*Adjusted for baseline, pooled center, and pooled center by treatment interaction

†p ≤0.05 vs. 30 mg daily pioglitazone + metformin

The therapeutic effect of pioglitazone in combination with metformin was observed in patients regardless of the metformin dose.

16 HOW SUPPLIED/STORAGE AND HANDLING

Pioglitazone and metformin hydrochloride tablets, USP are available in 15 mg pioglitazone (as the base)/500 mg metformin hydrochloride as follows:

Pioglitazone and metformin hydrochloride 15 mg/500 mg tablets are white, oval, biconvex, film-coated tablets with “SZ441” on one side and are supplied as follows:

NDC 70882-105-56, Package of 56 tablets (4 x 14 unit-of-dose blisters)

Storage

Store at 20° to 25° C (68° to 77°F) [see USP Controlled Room Temperature]. Keep container tightly closed, and protect from moisture and humidity.

17 PATIENT COUNSELING INFORMATION

See FDA-Approved Patient Labeling (Medication Guide)

- It is important to instruct patients to adhere to dietary instructions and to have blood glucose and glycosylated hemoglobin tested regularly. During periods of stress such as fever, trauma, infection, or surgery, medication requirements may change and patients should be reminded to seek medical advice promptly.
- Tell patients to promptly report any sign of macroscopic hematuria or other symptoms such as dysuria or urinary urgency that develop or increase during treatment as these may be due to bladder cancer.
- Explain to patients the risks of lactic acidosis, its symptoms and conditions that predispose to its development, as noted in the WARNINGS AND PRECAUTIONS (5.2) section. Advise patients to discontinue pioglitazone and metformin hydrochloride immediately and to promptly notify their healthcare professional if unexplained hyperventilation, myalgia, gastrointestinal symptoms, malaise, unusual somnolence, or other nonspecific symptoms occur.
- Counsel patients against excessive alcohol intake while receiving pioglitazone and metformin hydrochloride.
- Inform patients to immediately report symptoms of an unusually rapid increase in weight or edema, shortness of breath, or other symptoms of heart failure while receiving pioglitazone and metformin hydrochloride.
- Tell patients to promptly stop taking pioglitazone and metformin hydrochloride and seek immediate medical advice if there is unexplained nausea, vomiting, abdominal pain, fatigue, anorexia, or dark urine as these symptoms may be due to hepatotoxicity.
- Inform patients about the importance of regular testing of renal function and hematologic parameters when receiving treatment with pioglitazone and metformin hydrochloride.
- Inform patients that therapy with a thiazolidinedione, which is the active pioglitazone component of the pioglitazone and metformin hydrochloride tablet, may result in ovulation in some premenopausal anovulatory women. As a result, these patients may be at an increased risk for pregnancy while taking pioglitazone and metformin hydrochloride. Recommend adequate contraception for all pre-menopausal women who are prescribed pioglitazone and metformin hydrochloride.
- Patients should be advised to notify their health practitioner or call the Poison Control Center immediately in case of pioglitazone and metformin hydrochloride overdose.
- Combination antihyperglycemic therapy may cause hypoglycemia. When initiating pioglitazone and metformin hydrochloride, the risks of hypoglycemia, its symptoms and treatment, and conditions that predispose to its development should be explained to patients and their family members.
- Patients should be told to take pioglitazone and metformin hydrochloride as prescribed and instructed that any change in dosing should only be done if directed by their physician. If a dose is missed on one day, the dose should not be doubled the following day.

For FDA-Approved Medication Guide
Refer to the medication guide provided separately in a pad.

Manufactured for Cambridge Therapeutic Technologies, Teaneck, NJ 07666
by Lek Pharmaceuticals d.d., SI-1526 Ljubljana, Slovenia

Packaged by Legacy Pharmaceutical Packaging, LLC
Earth City, MO 63045

Revised November 2016

20479